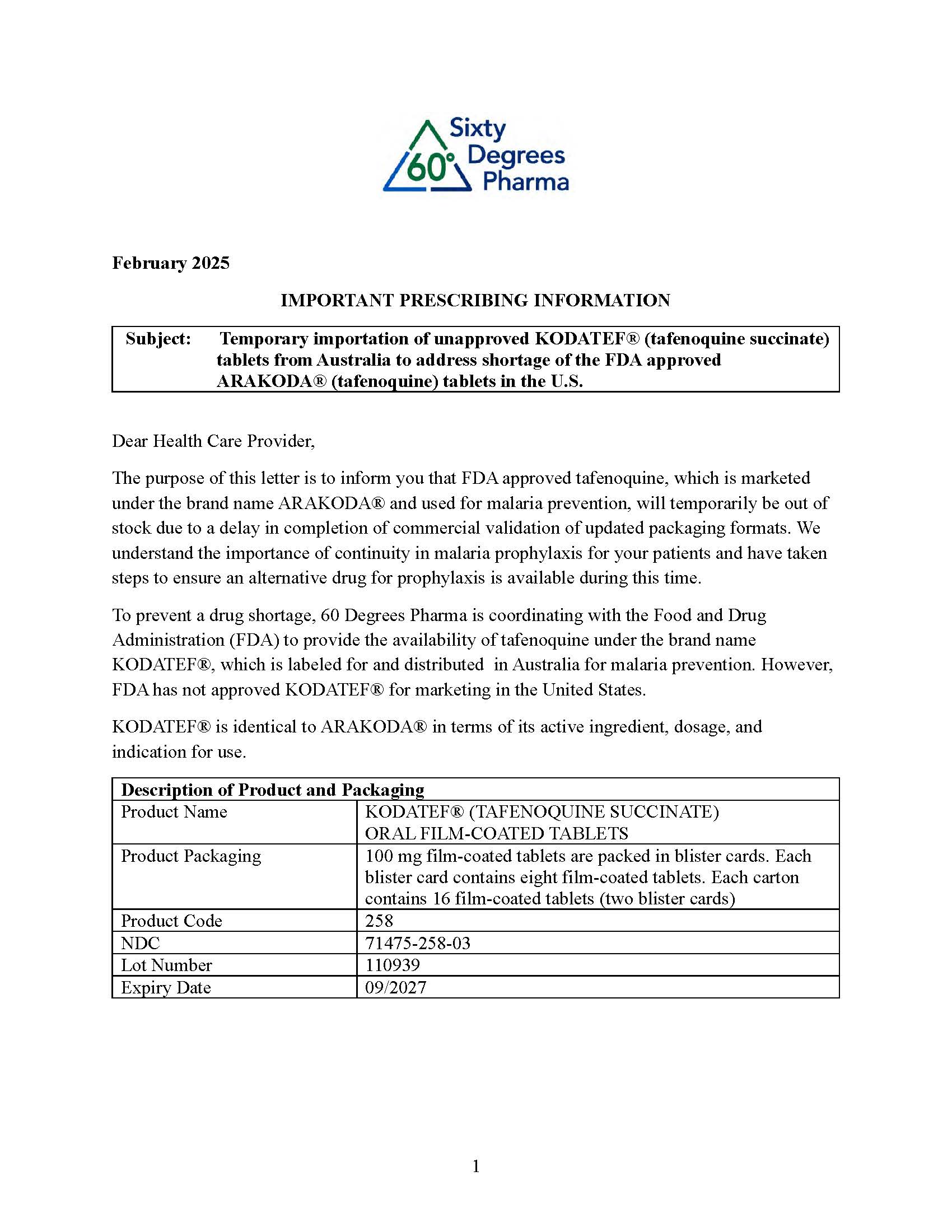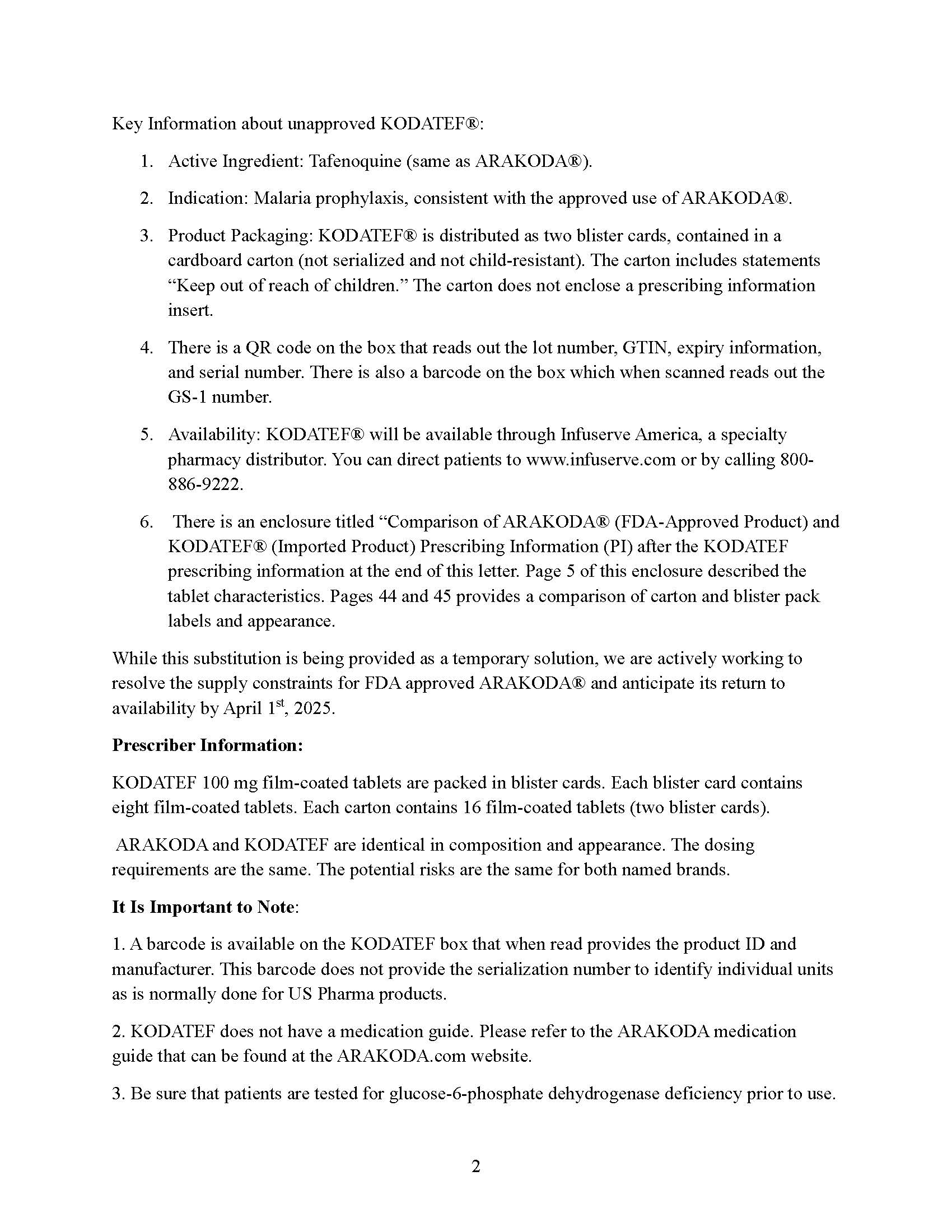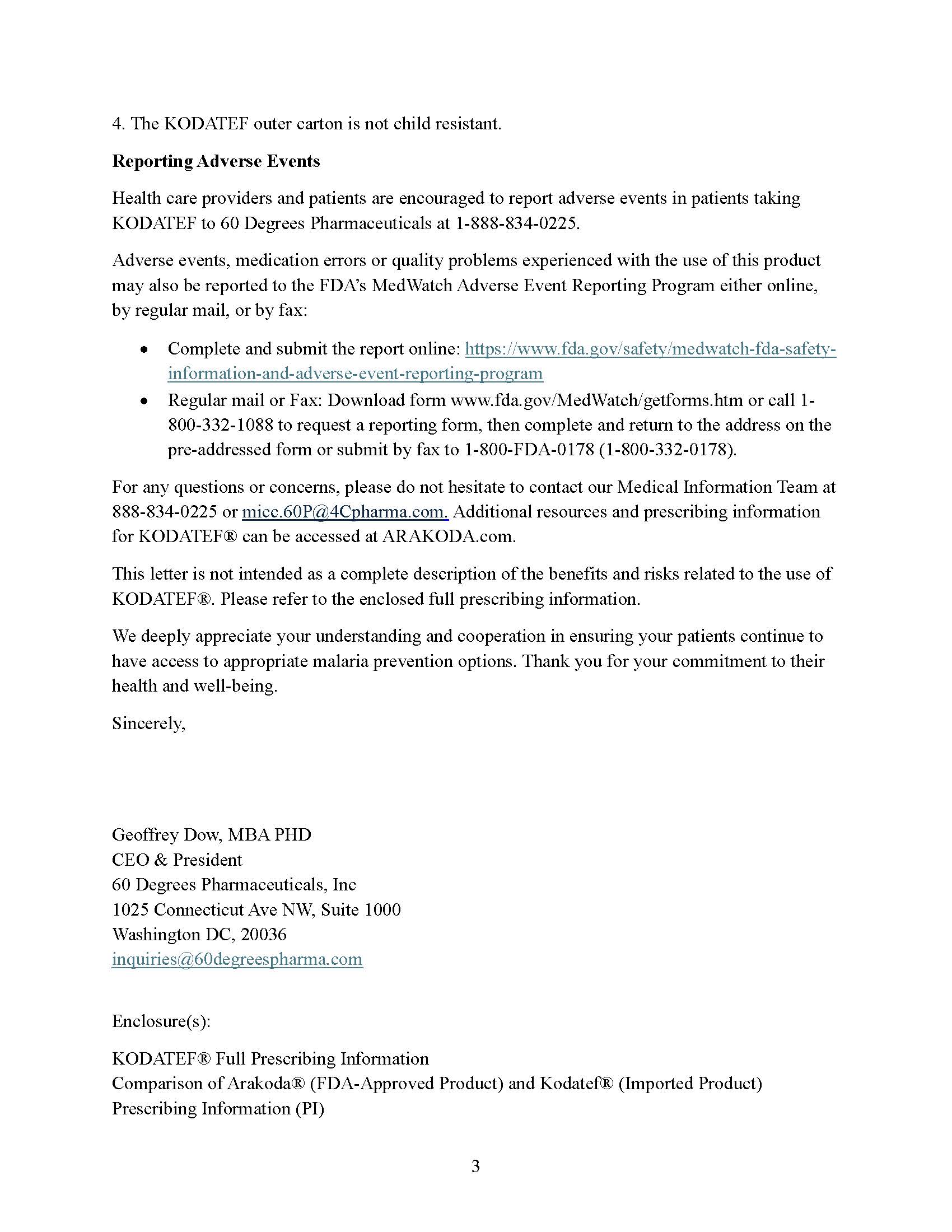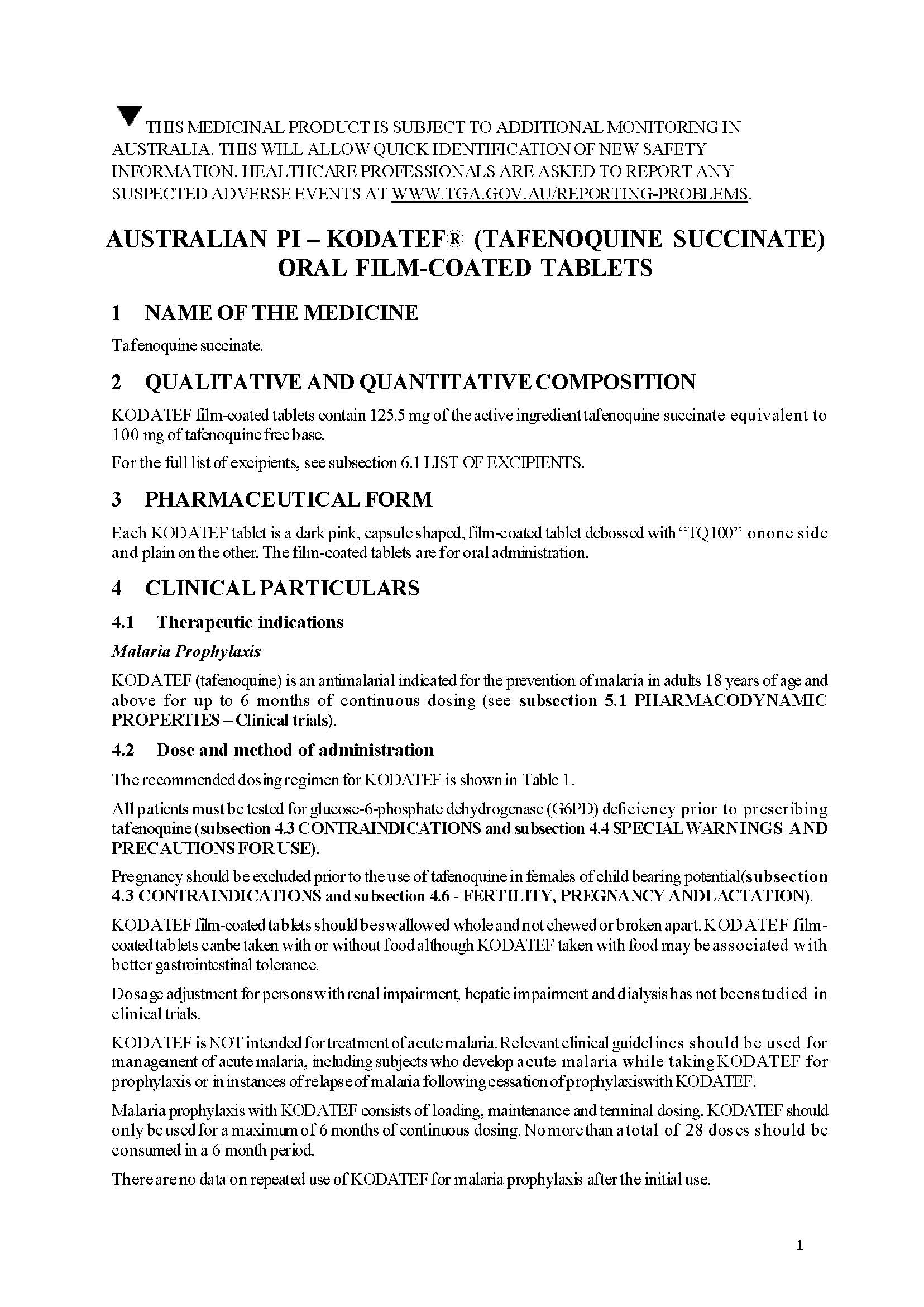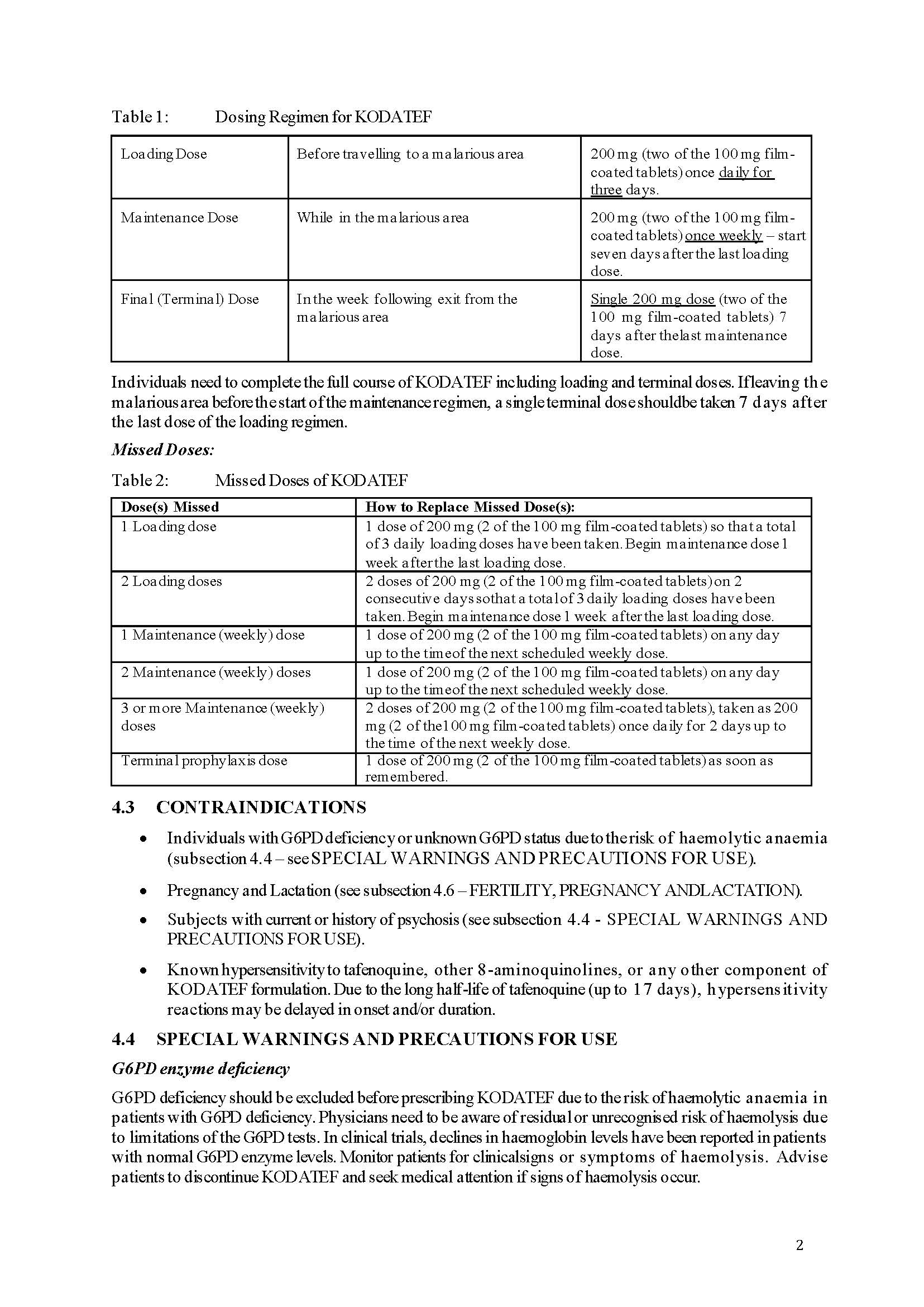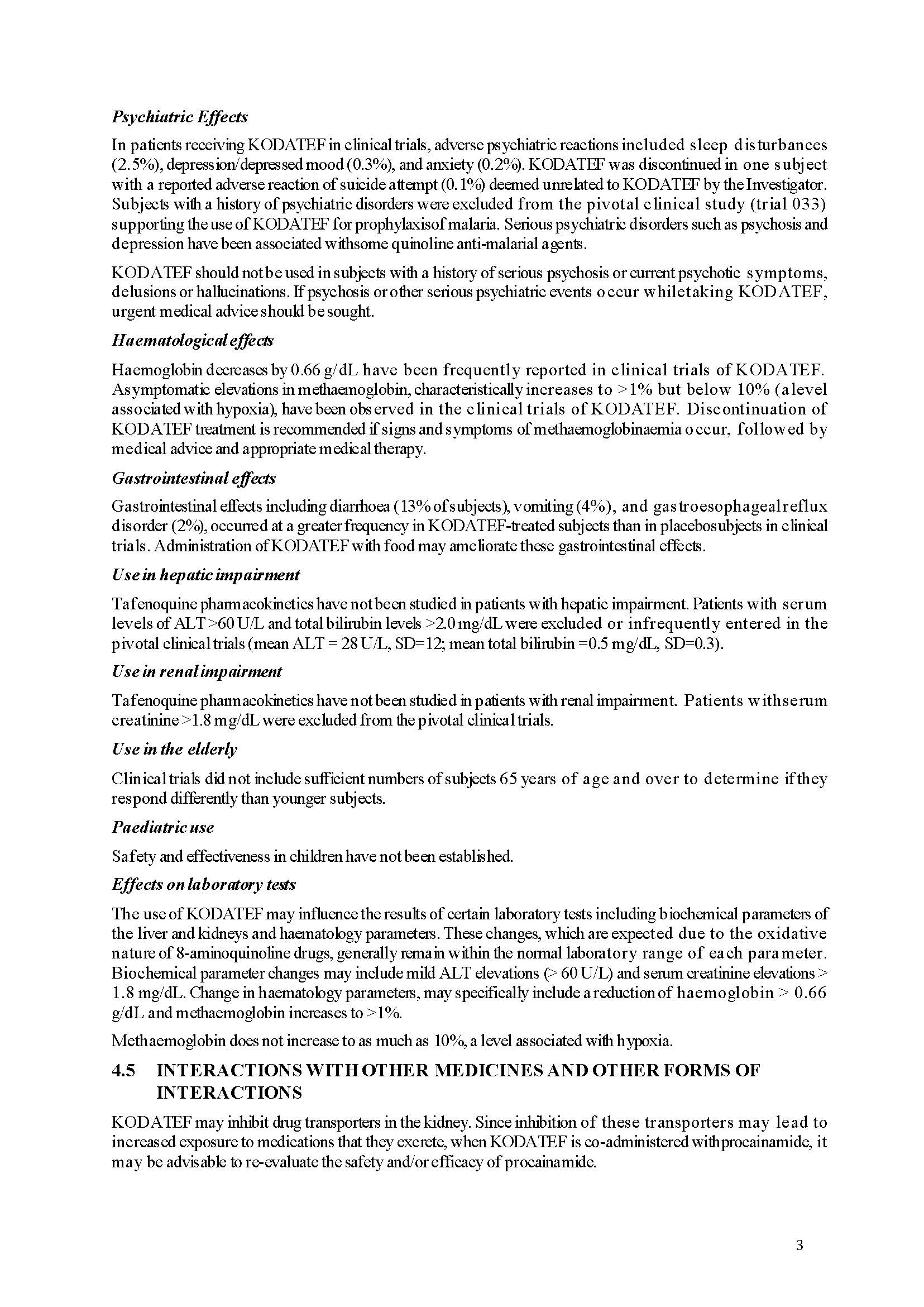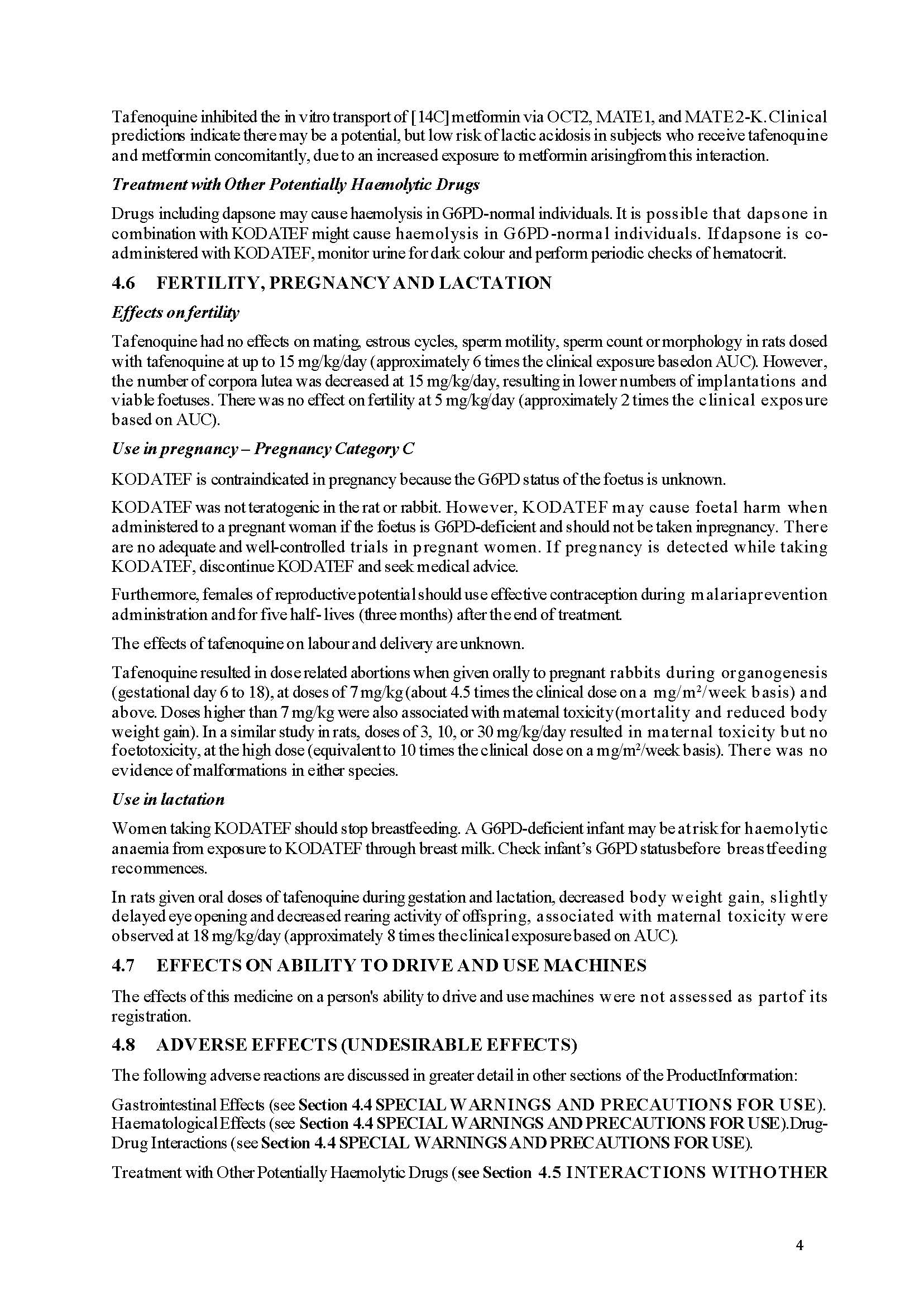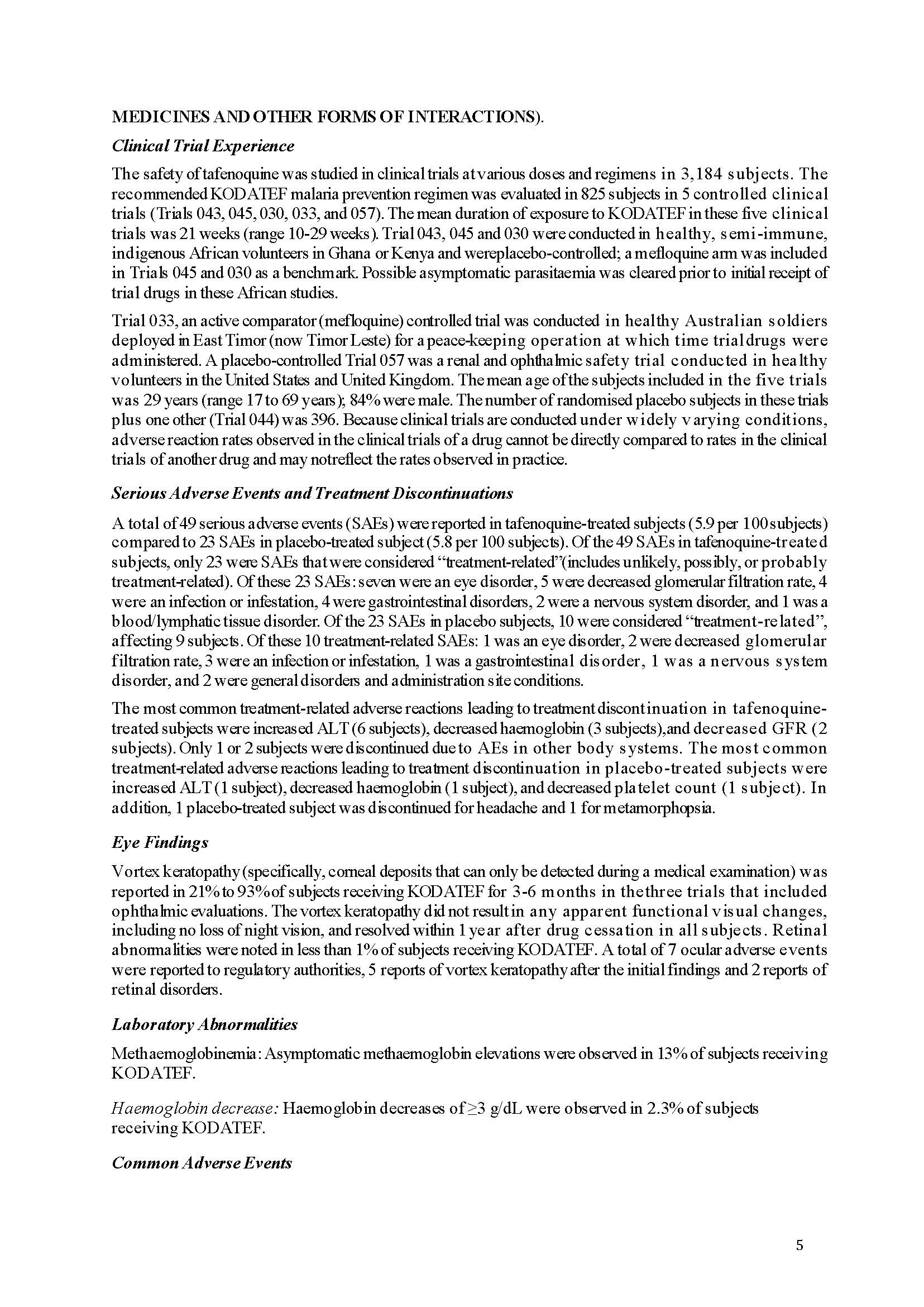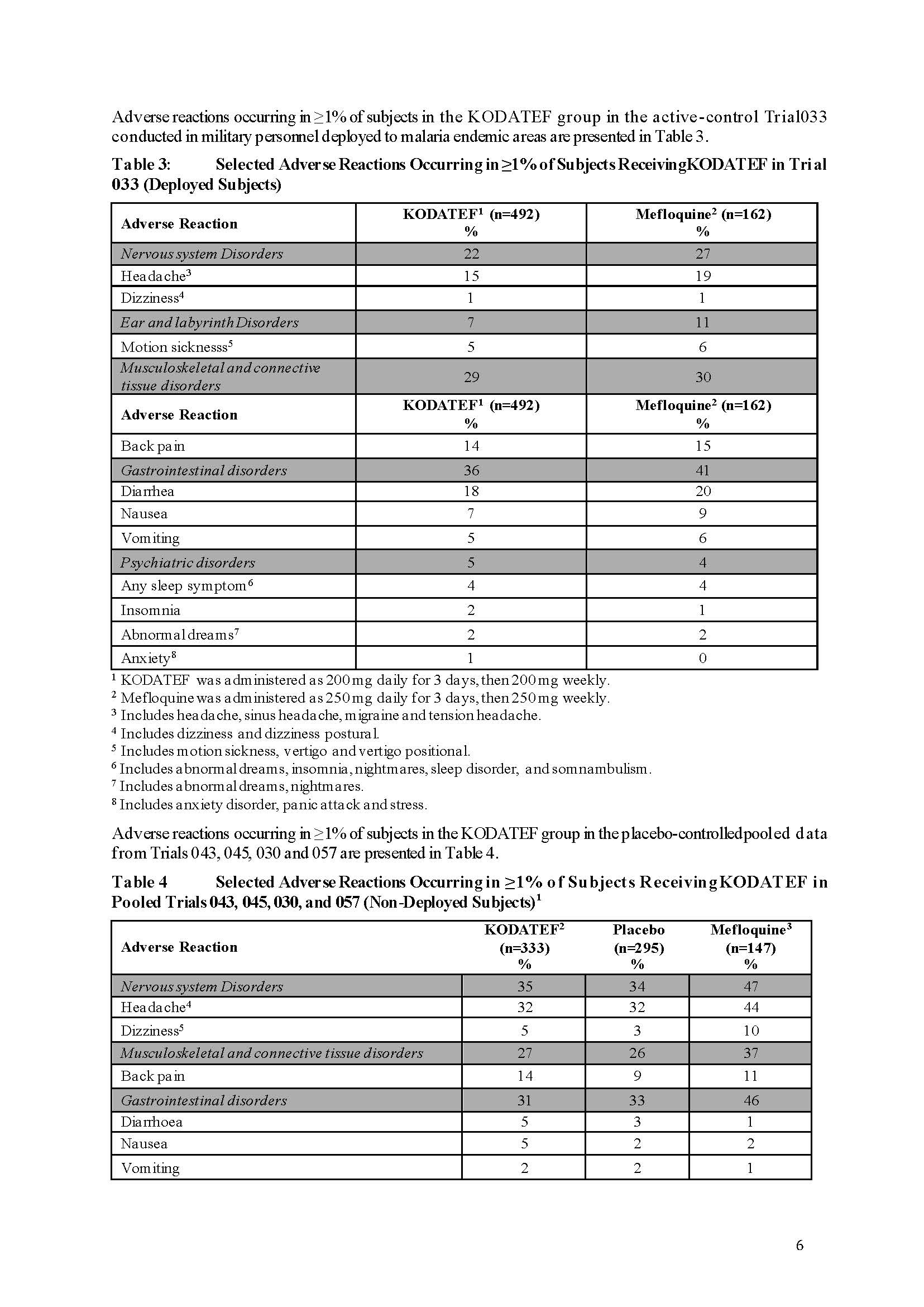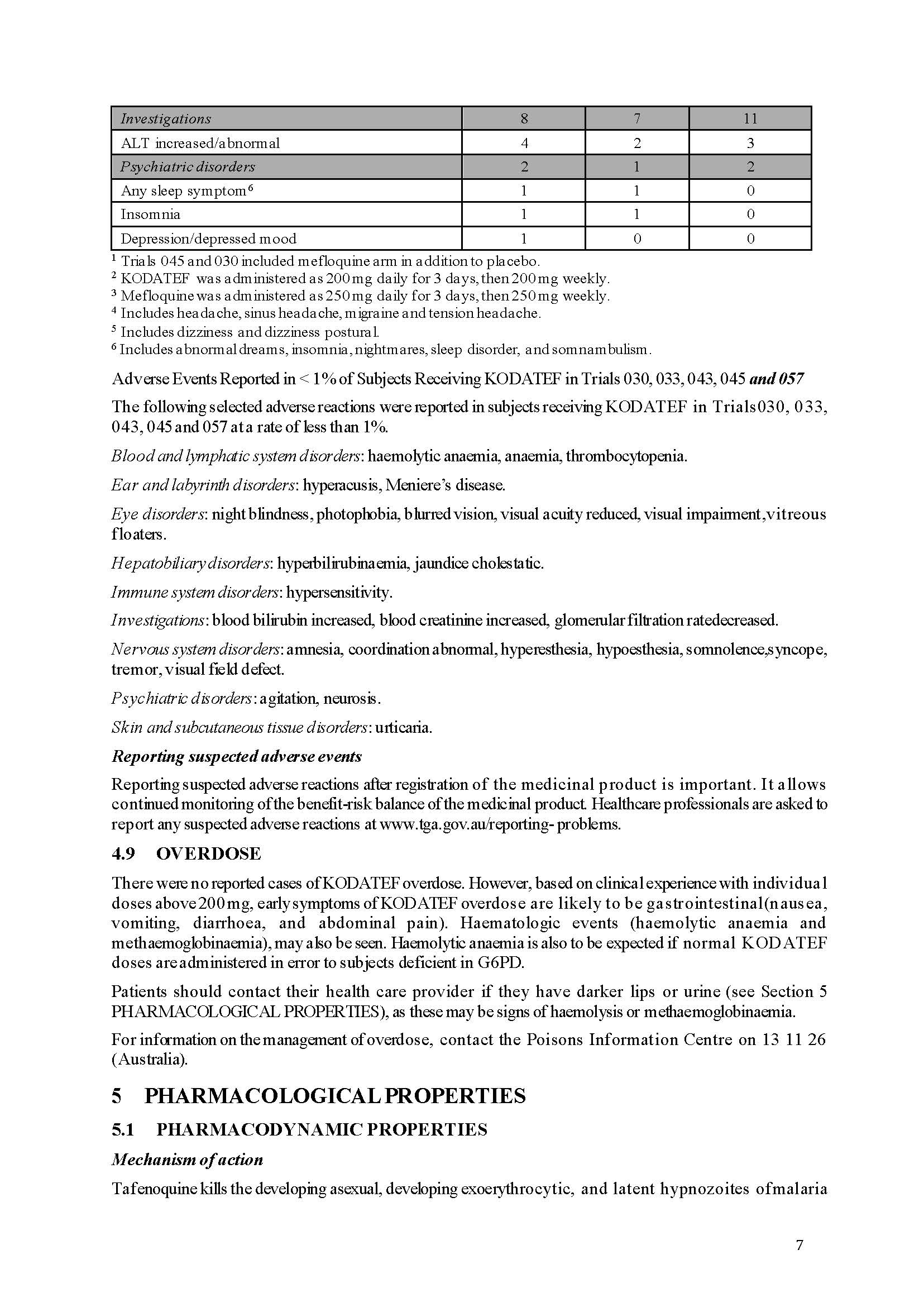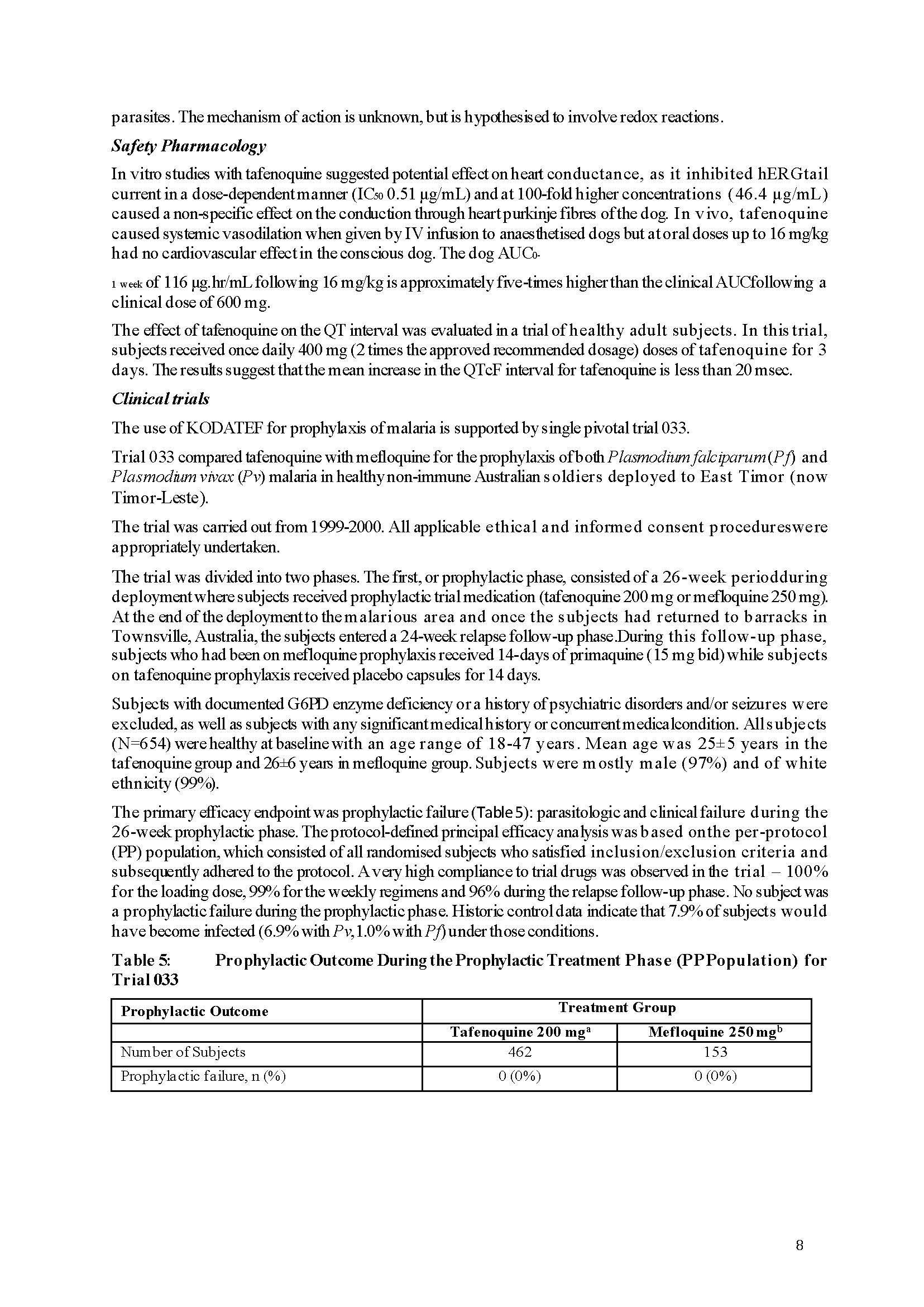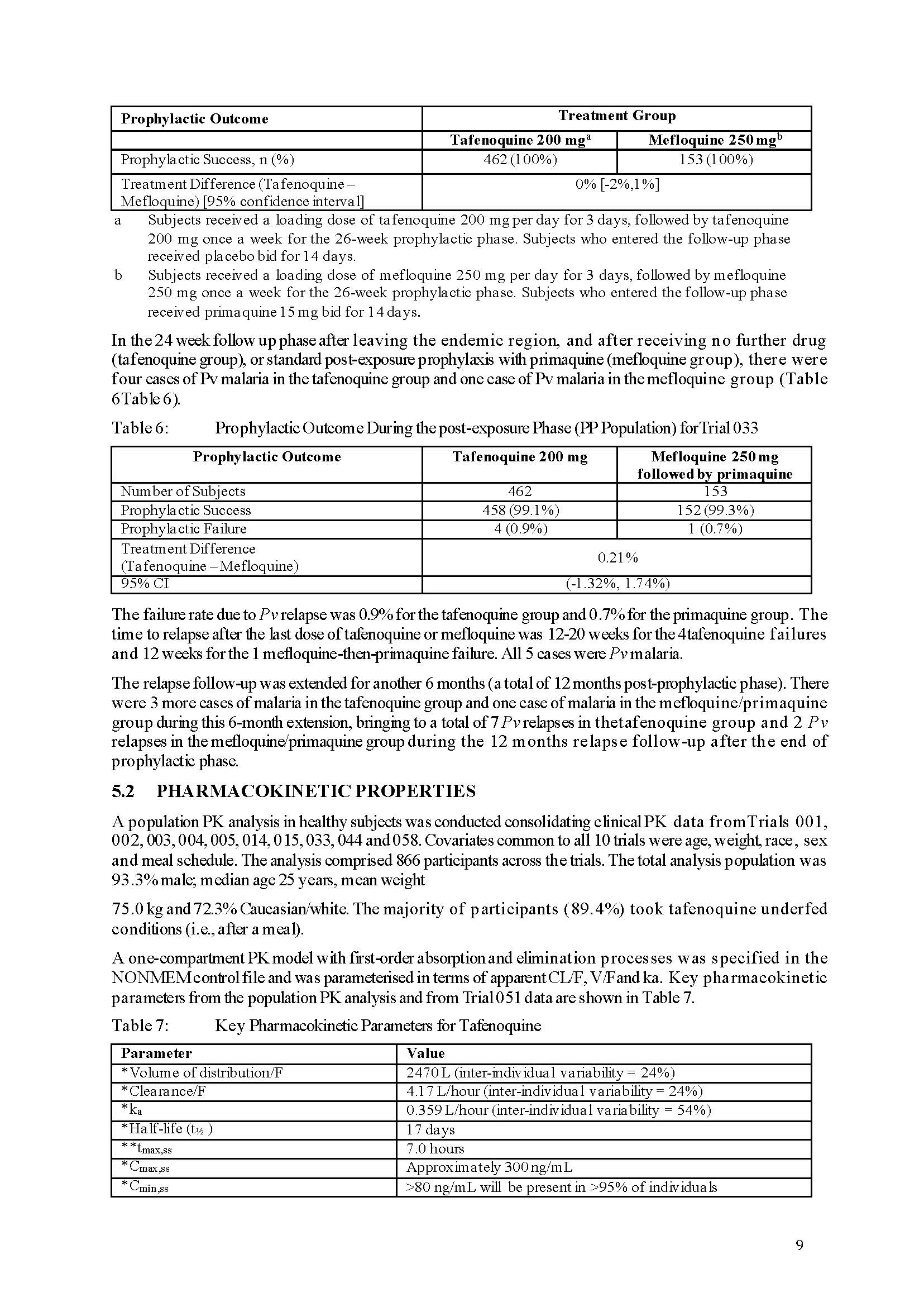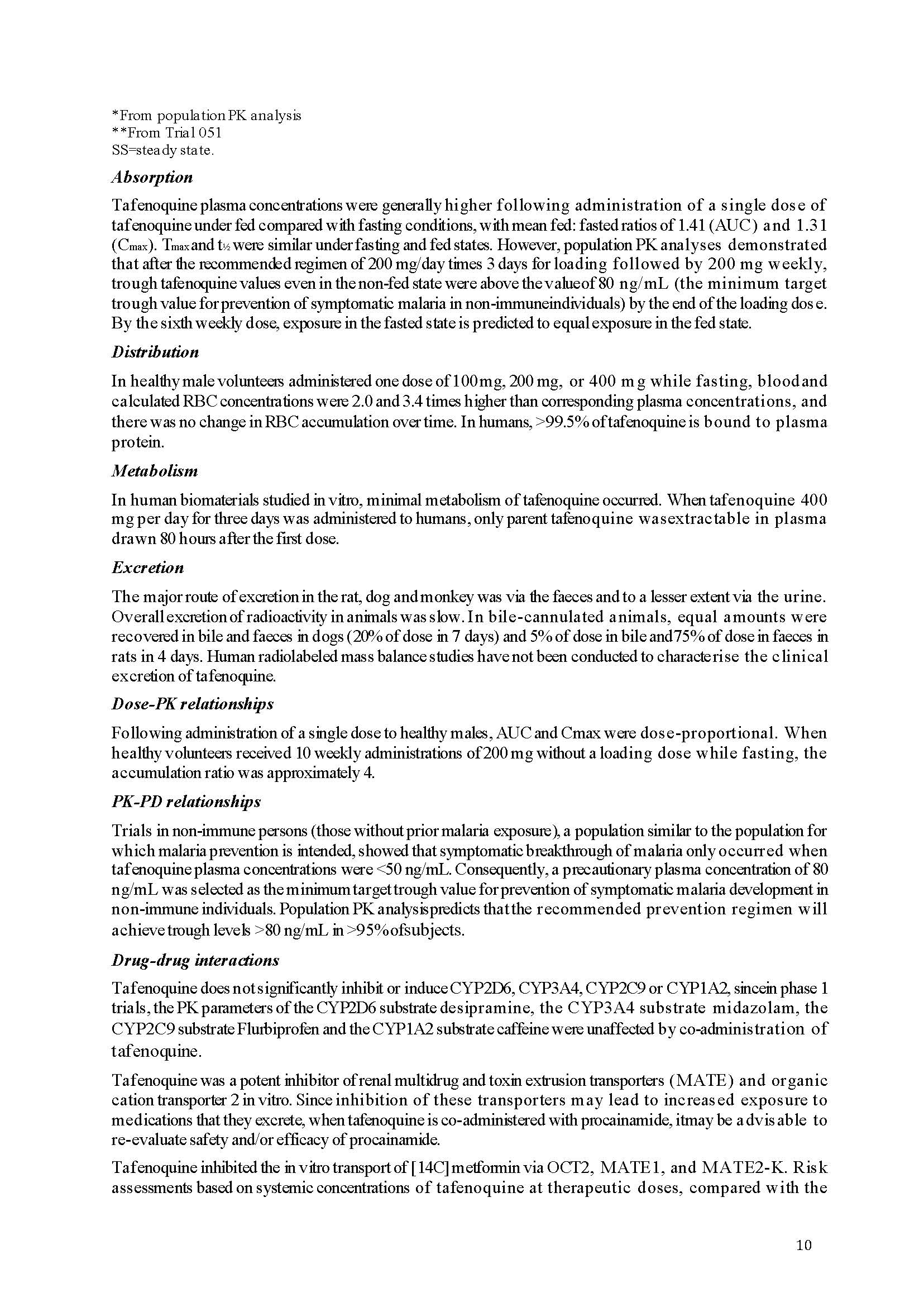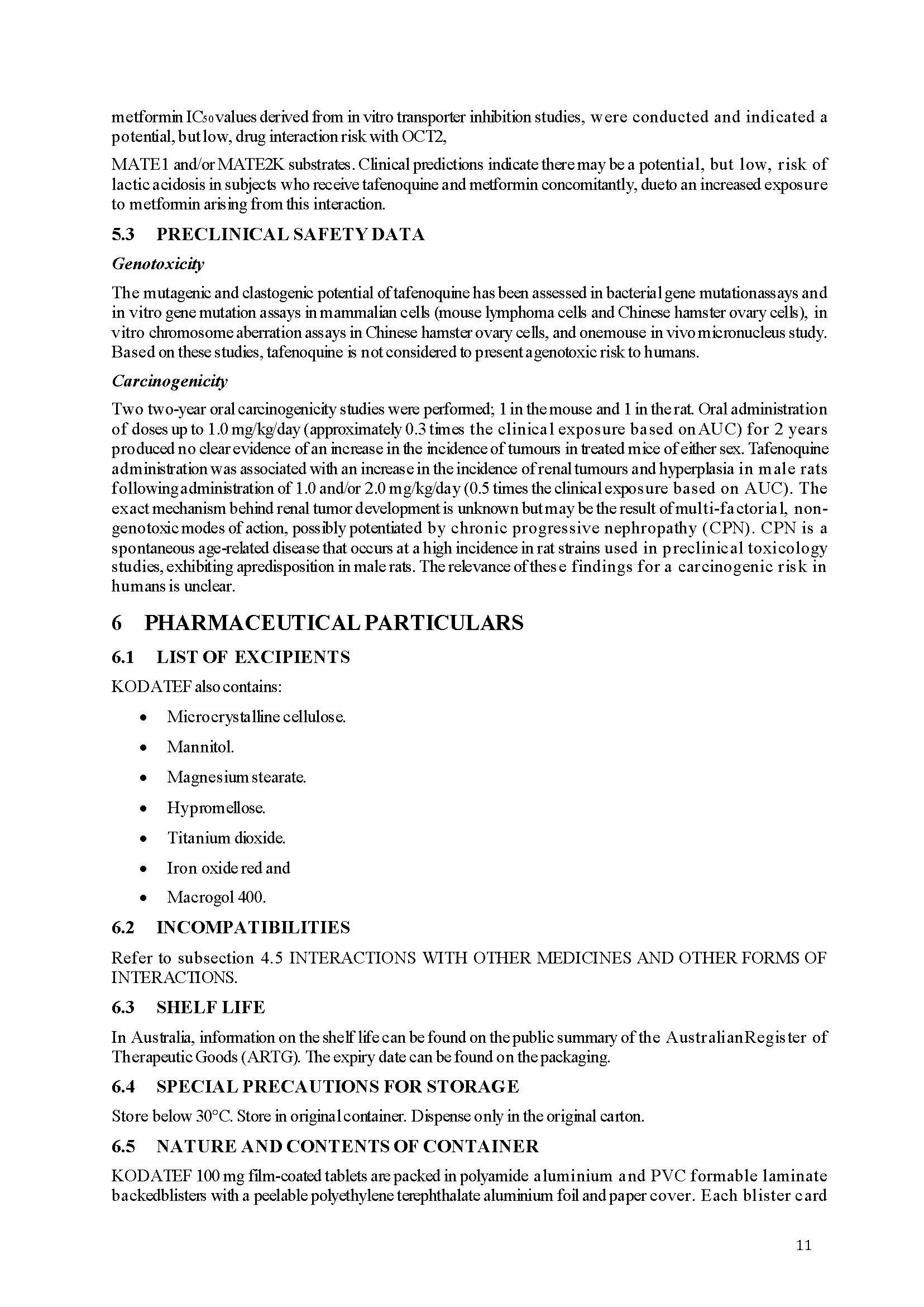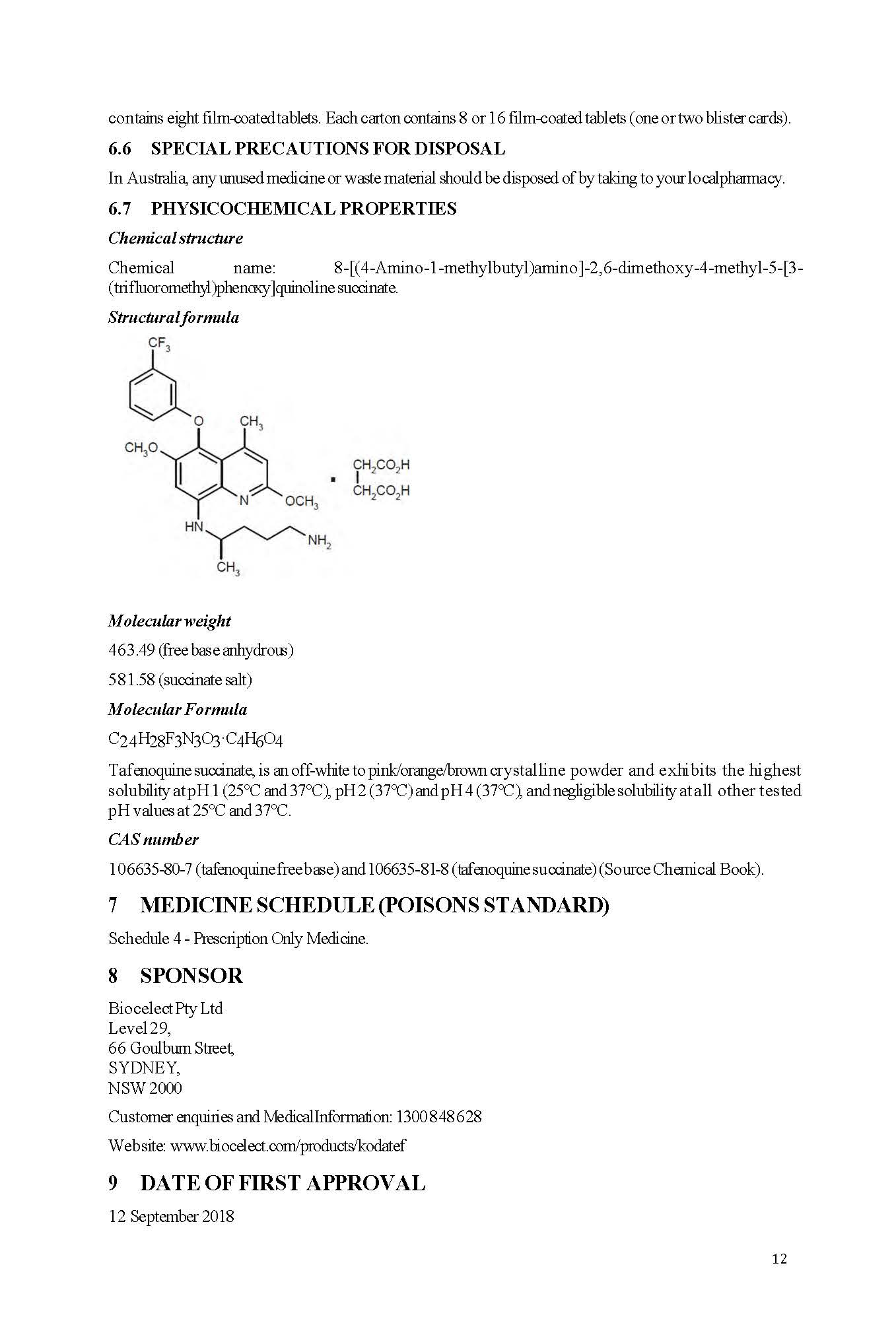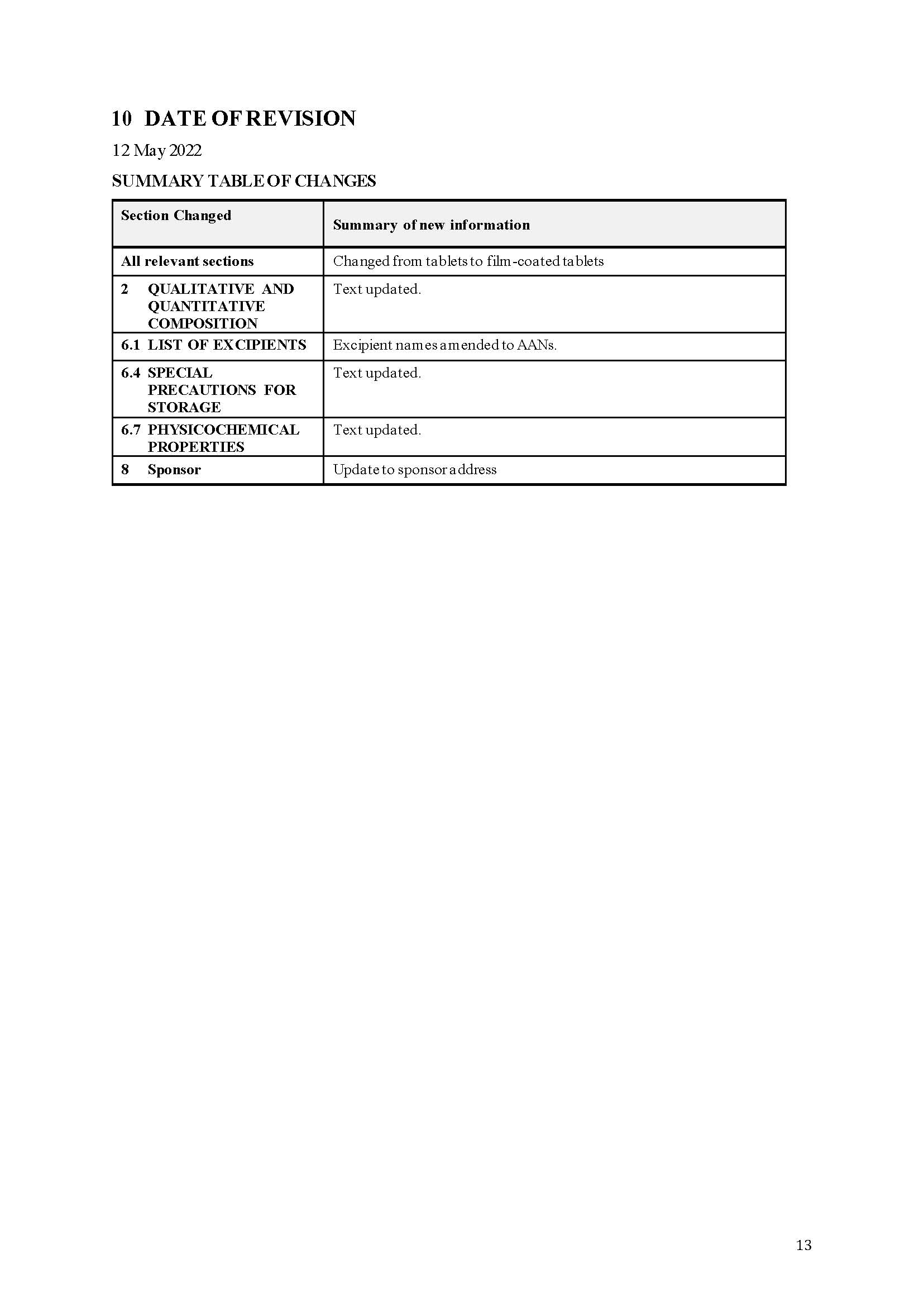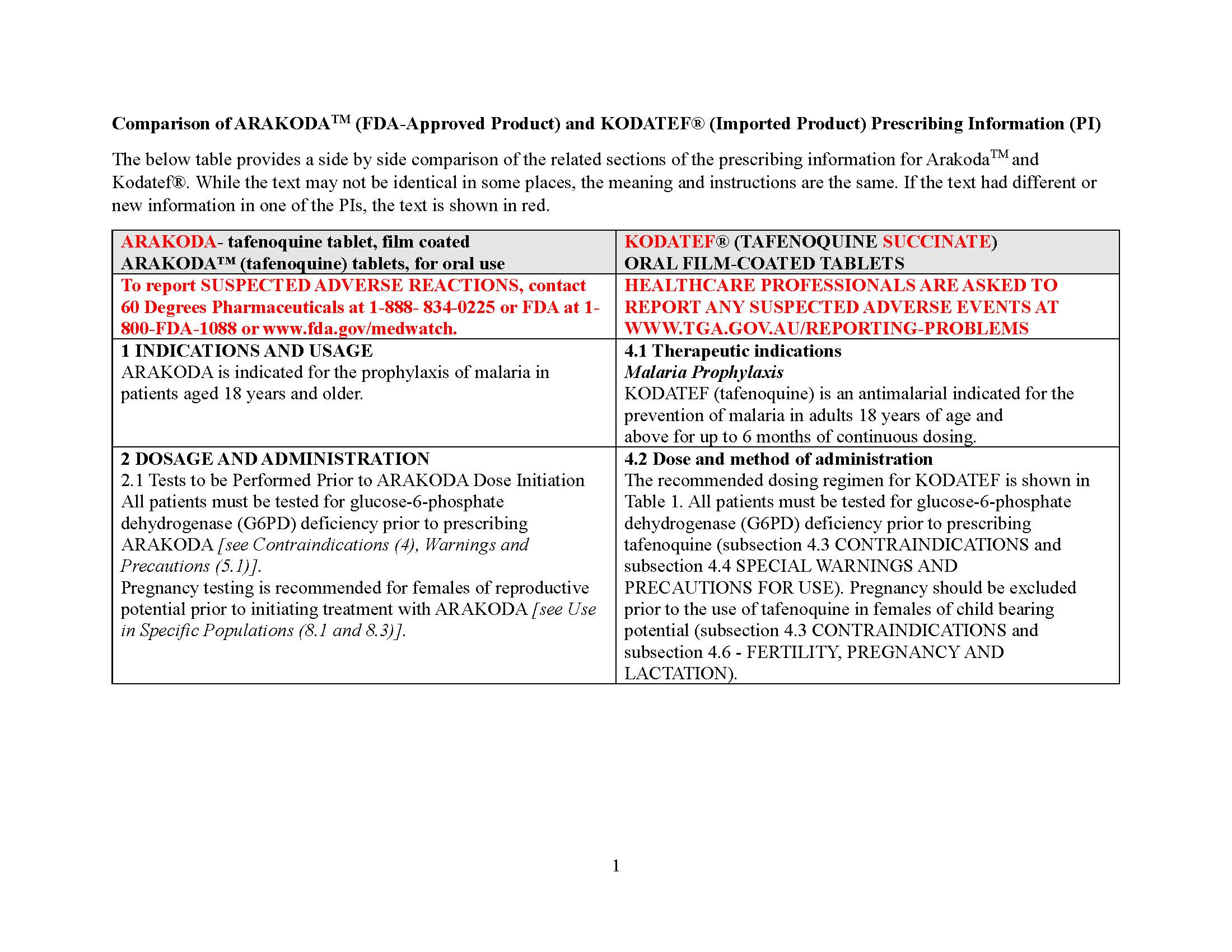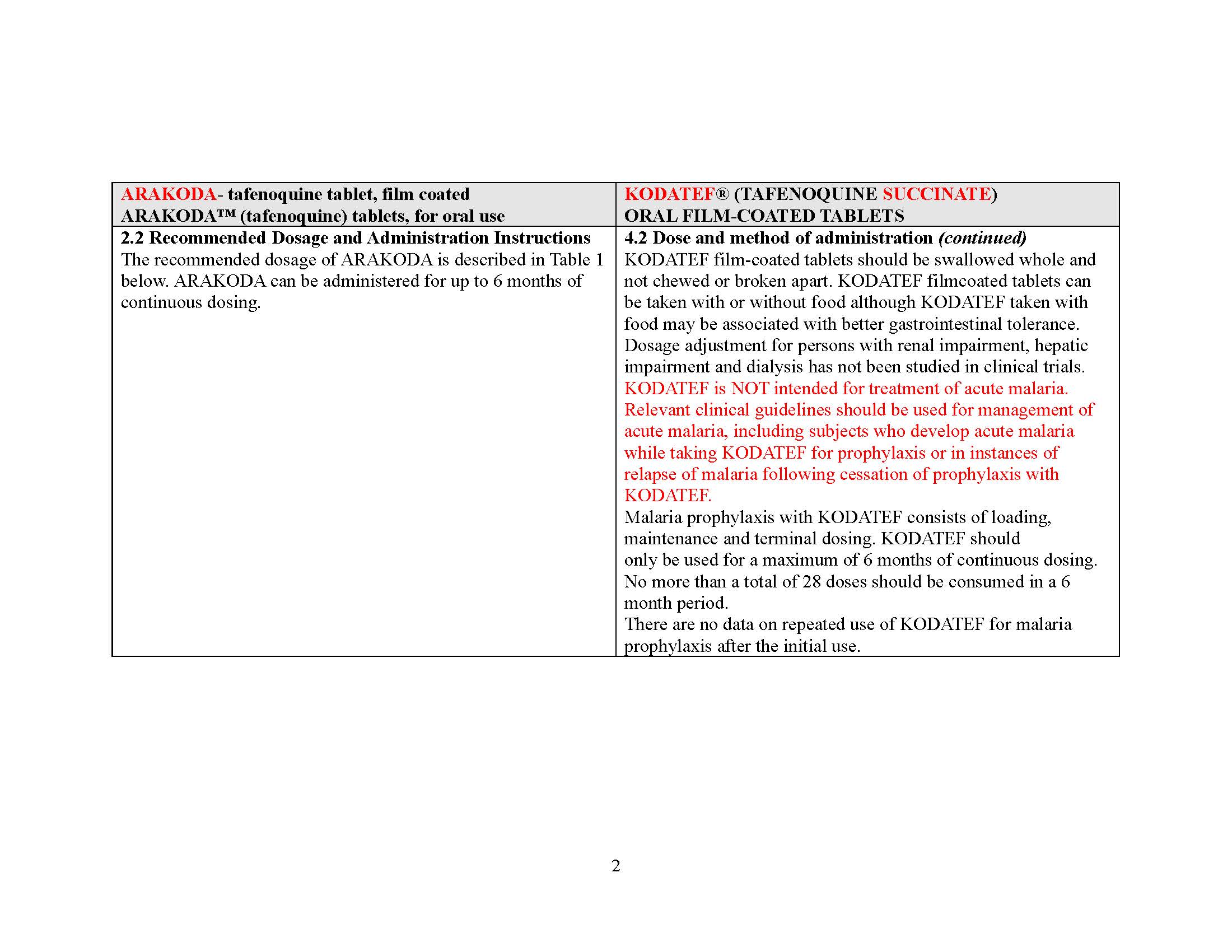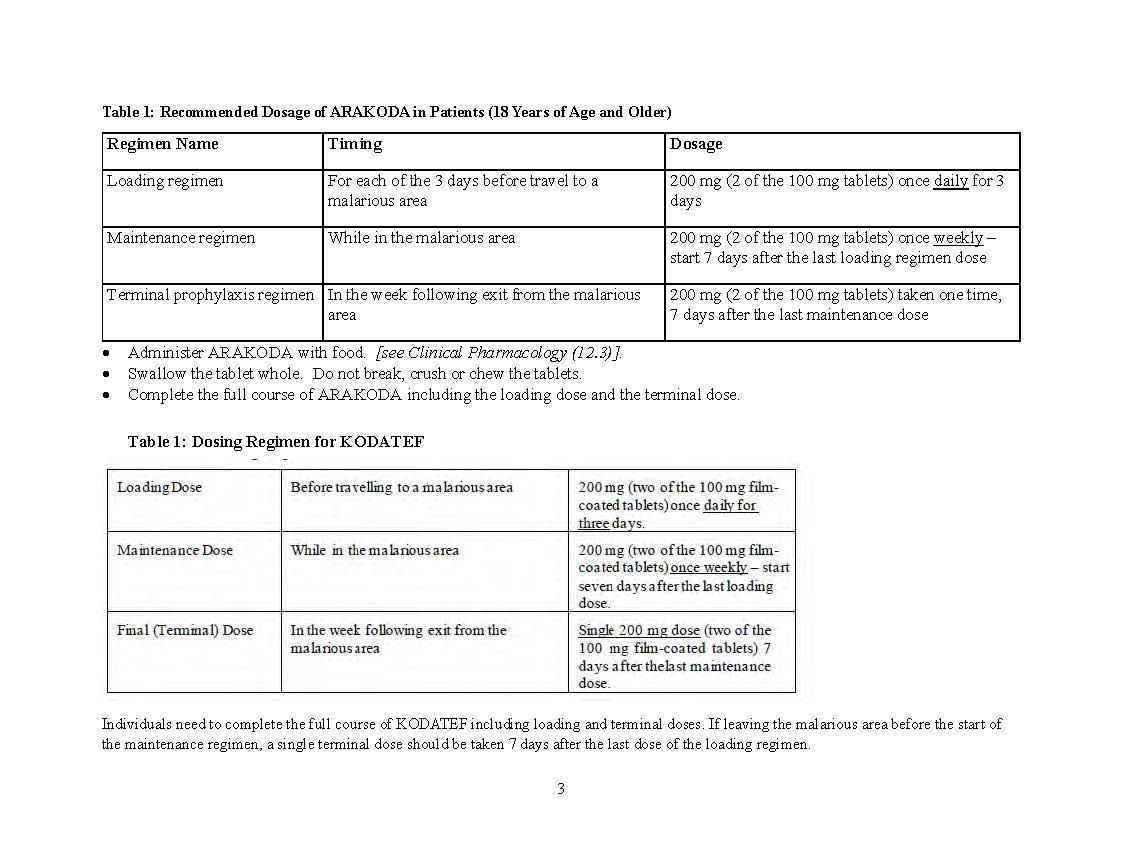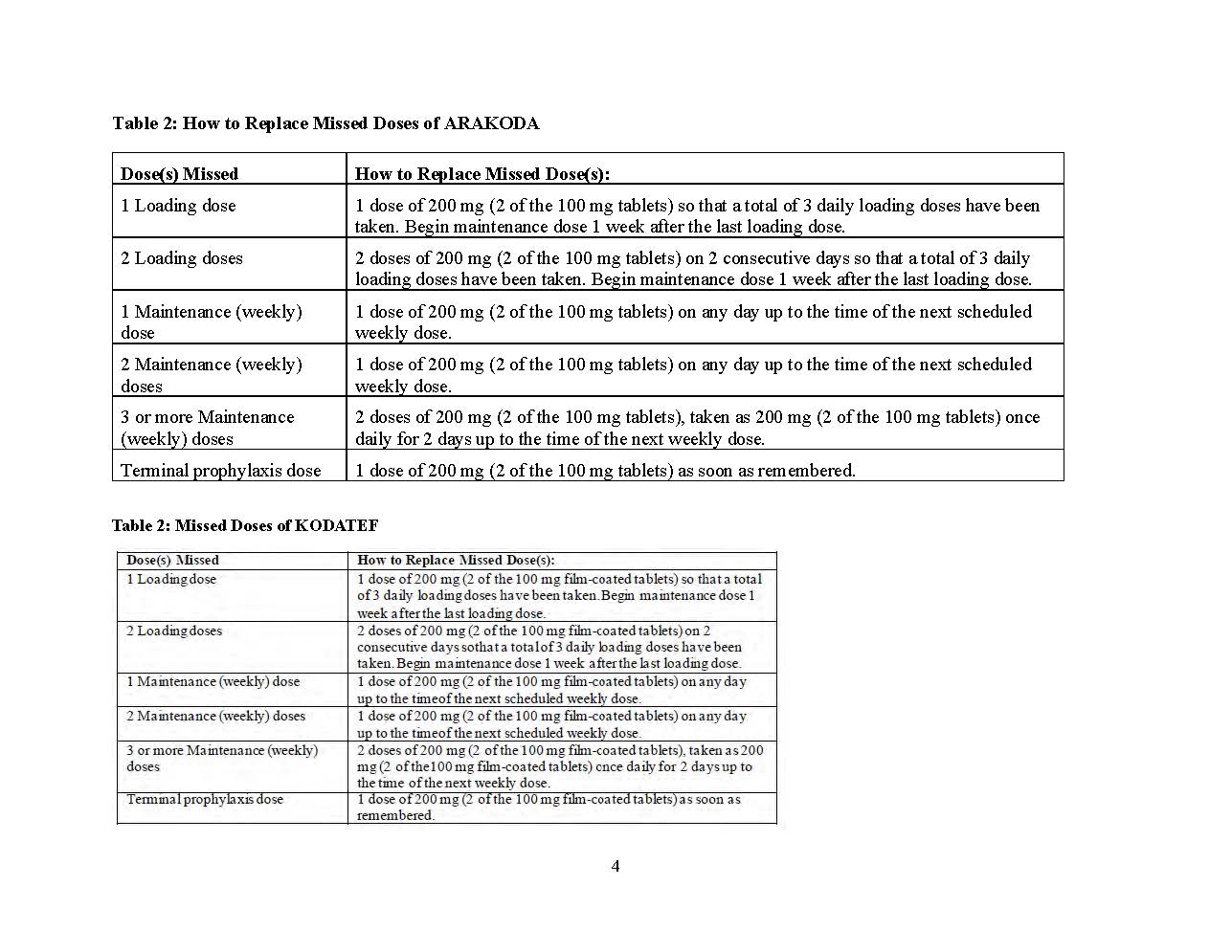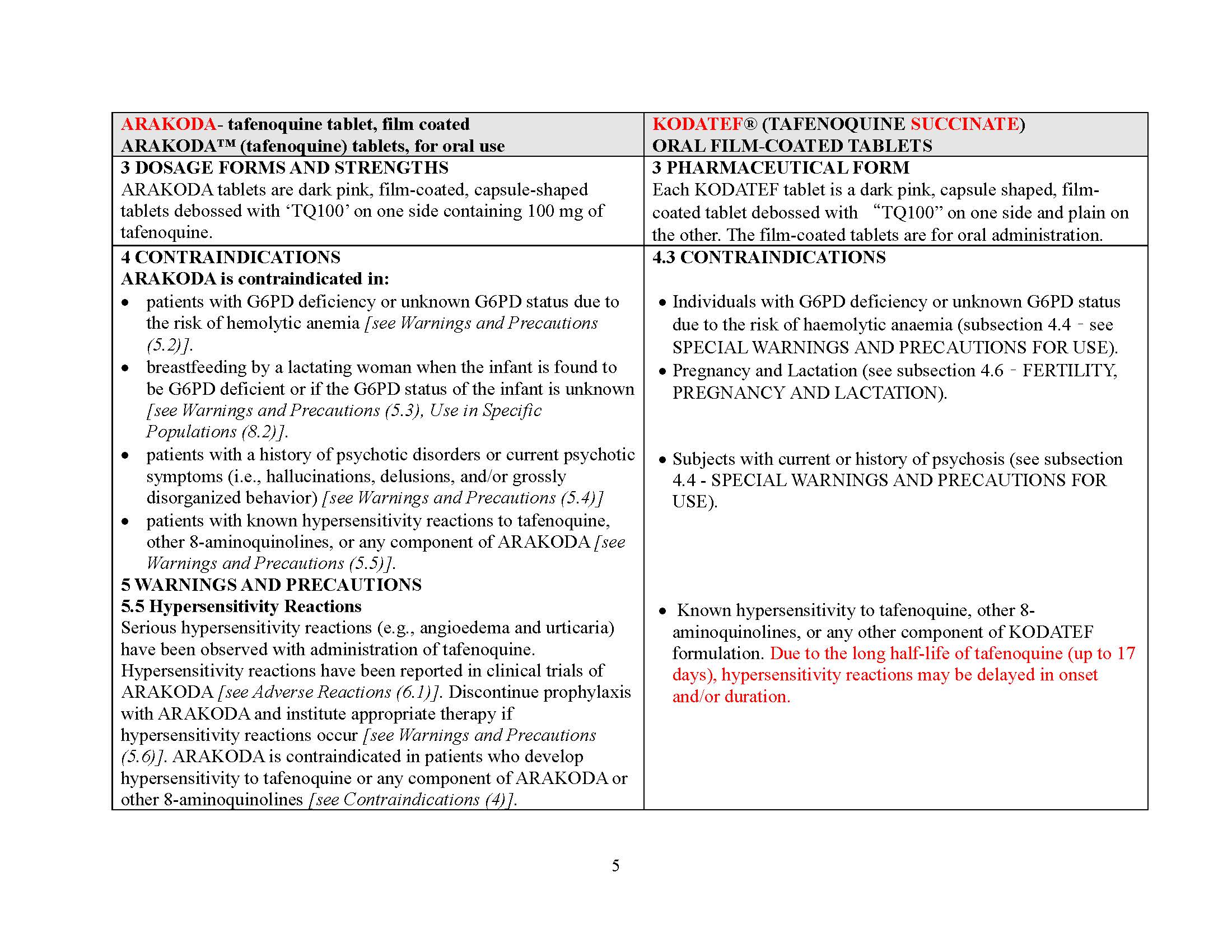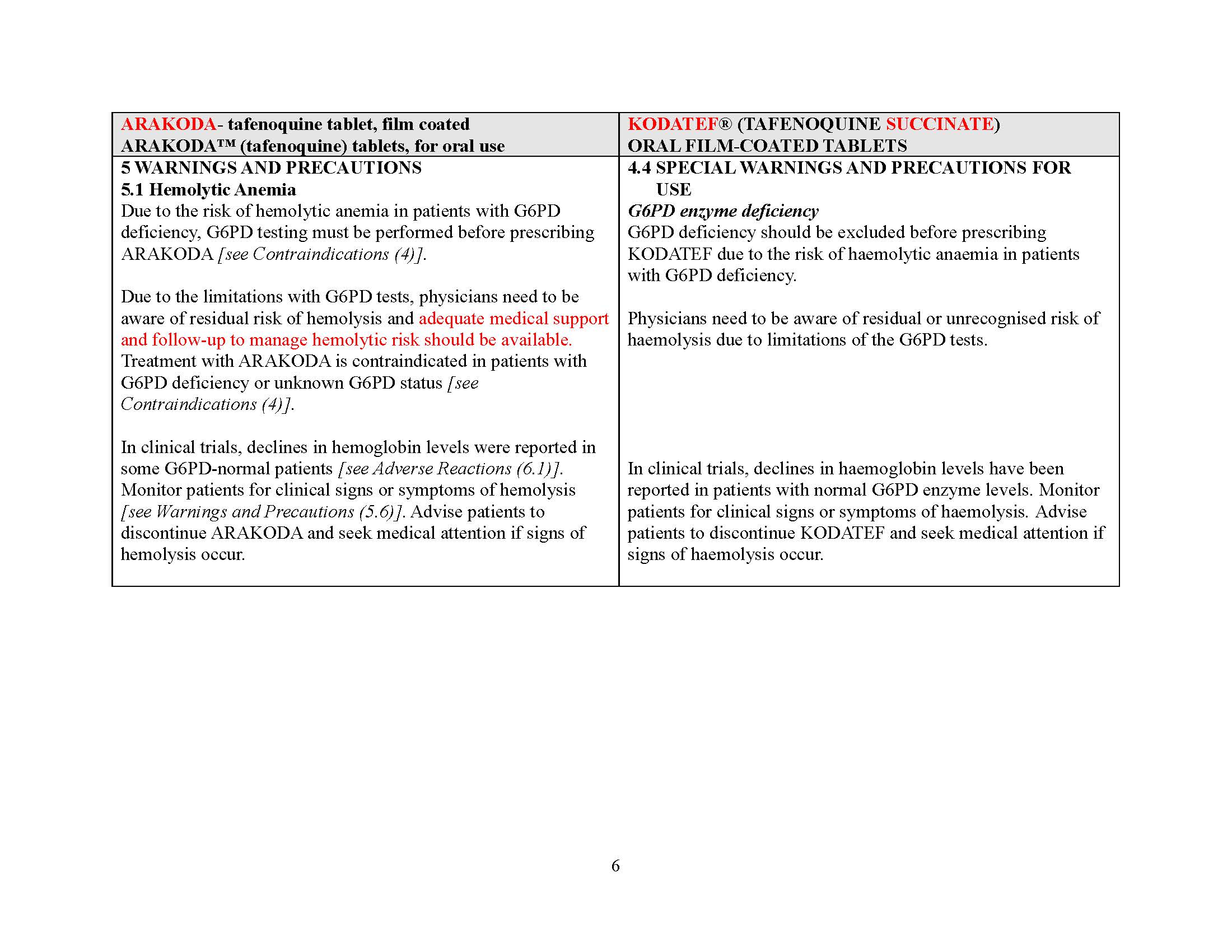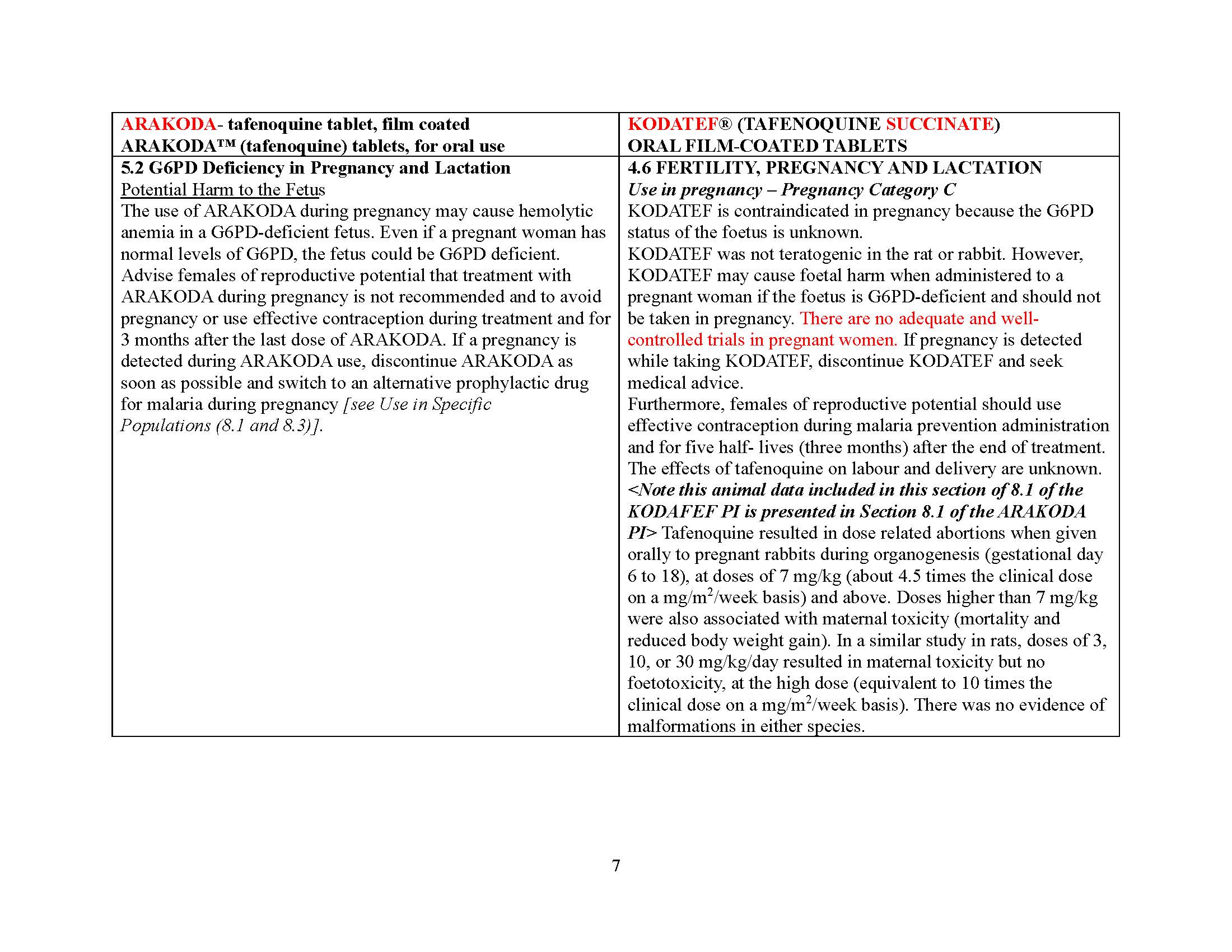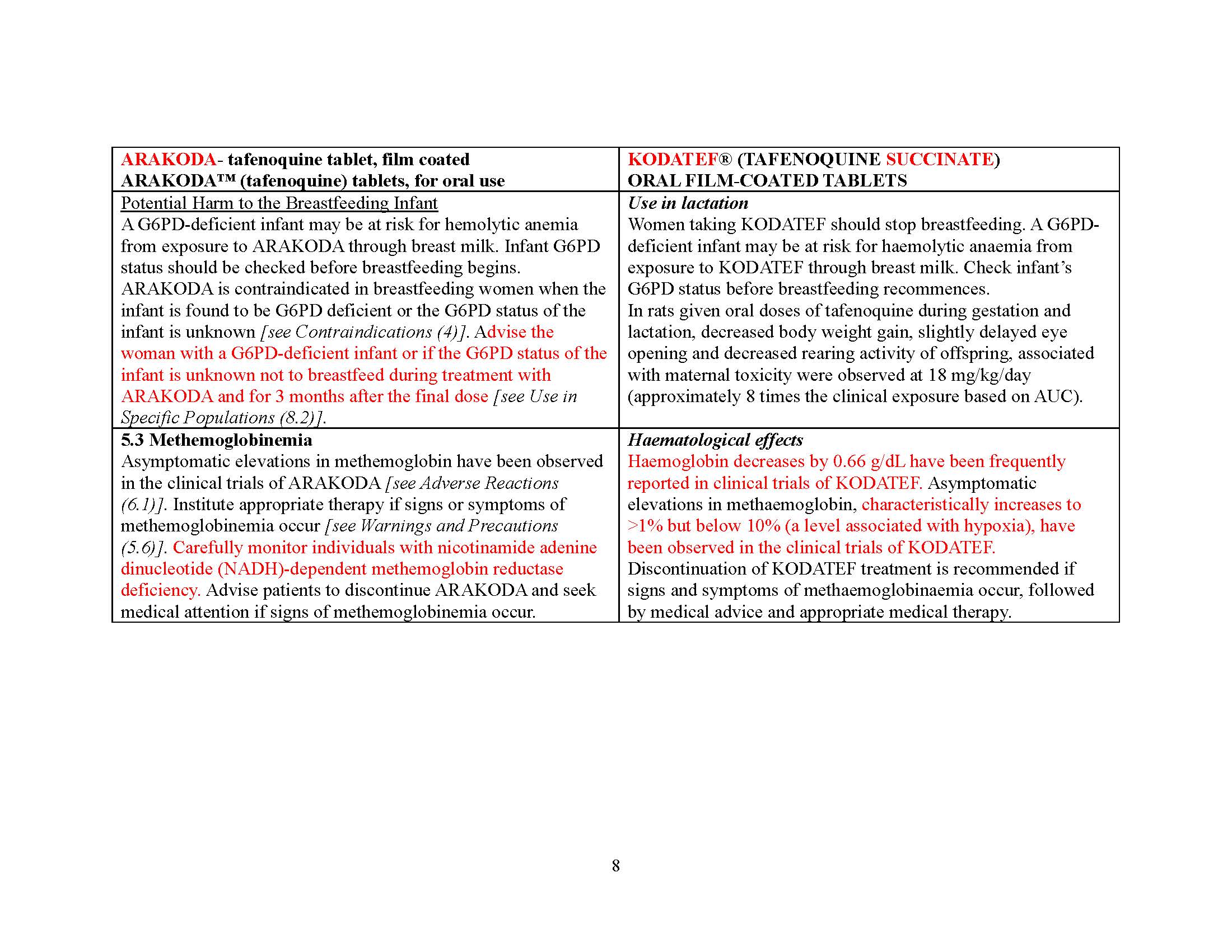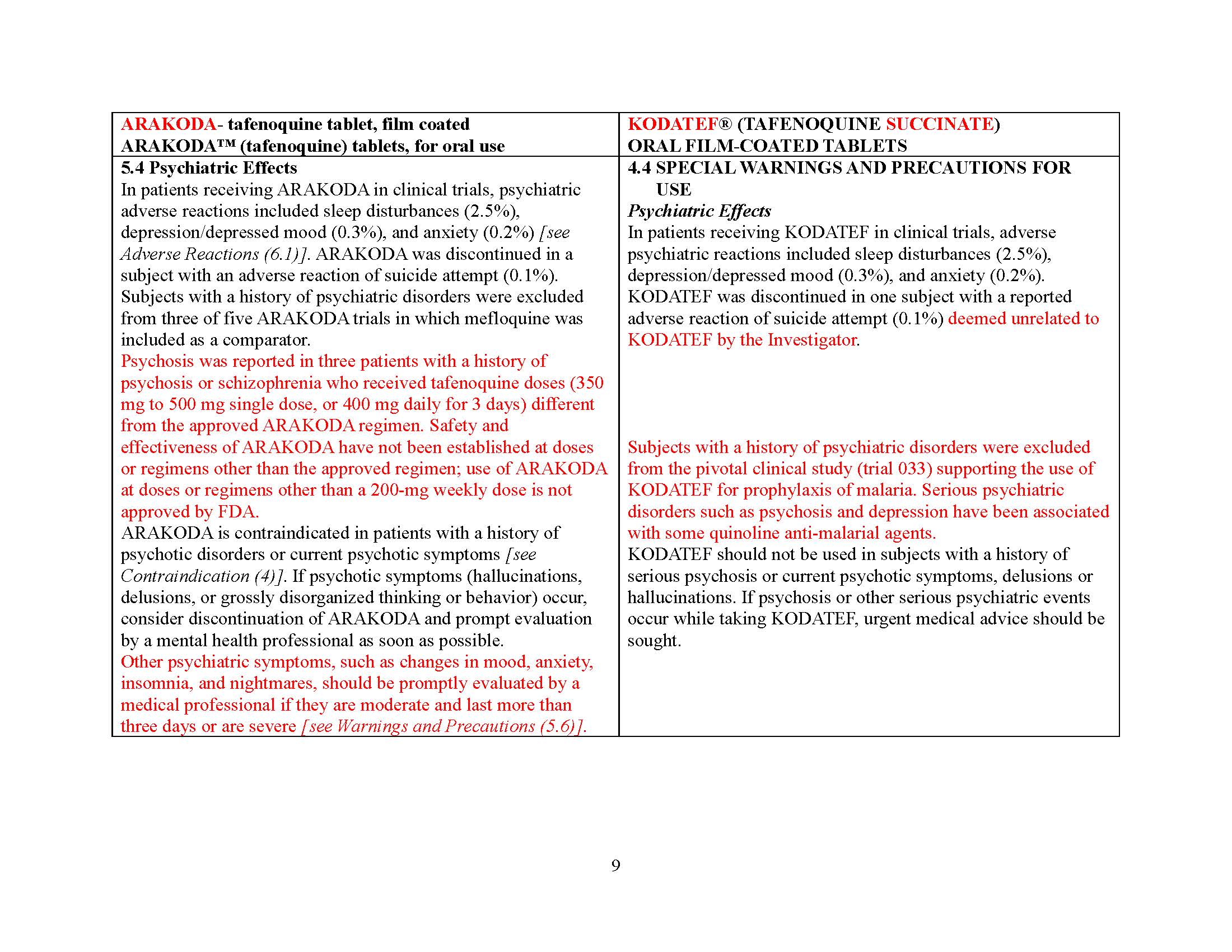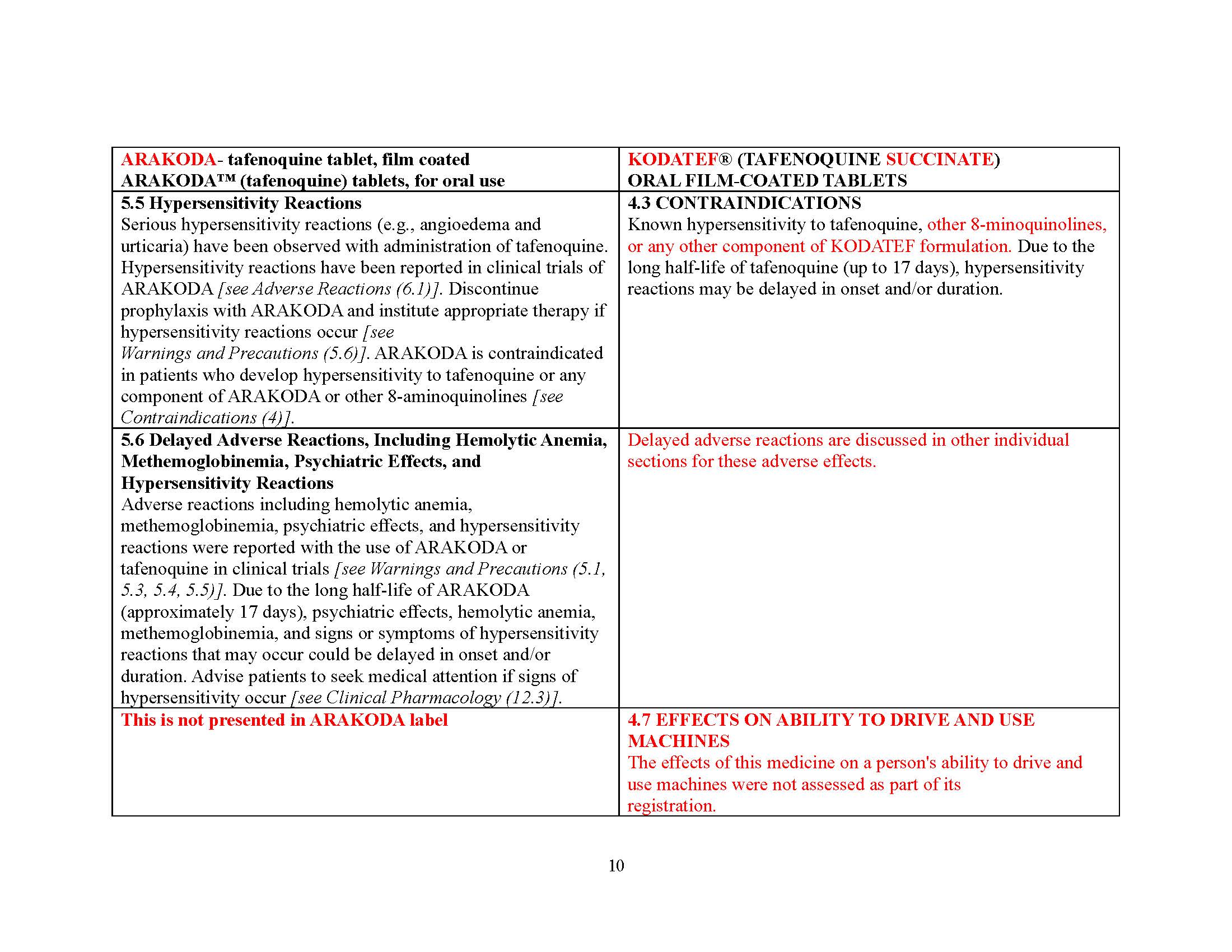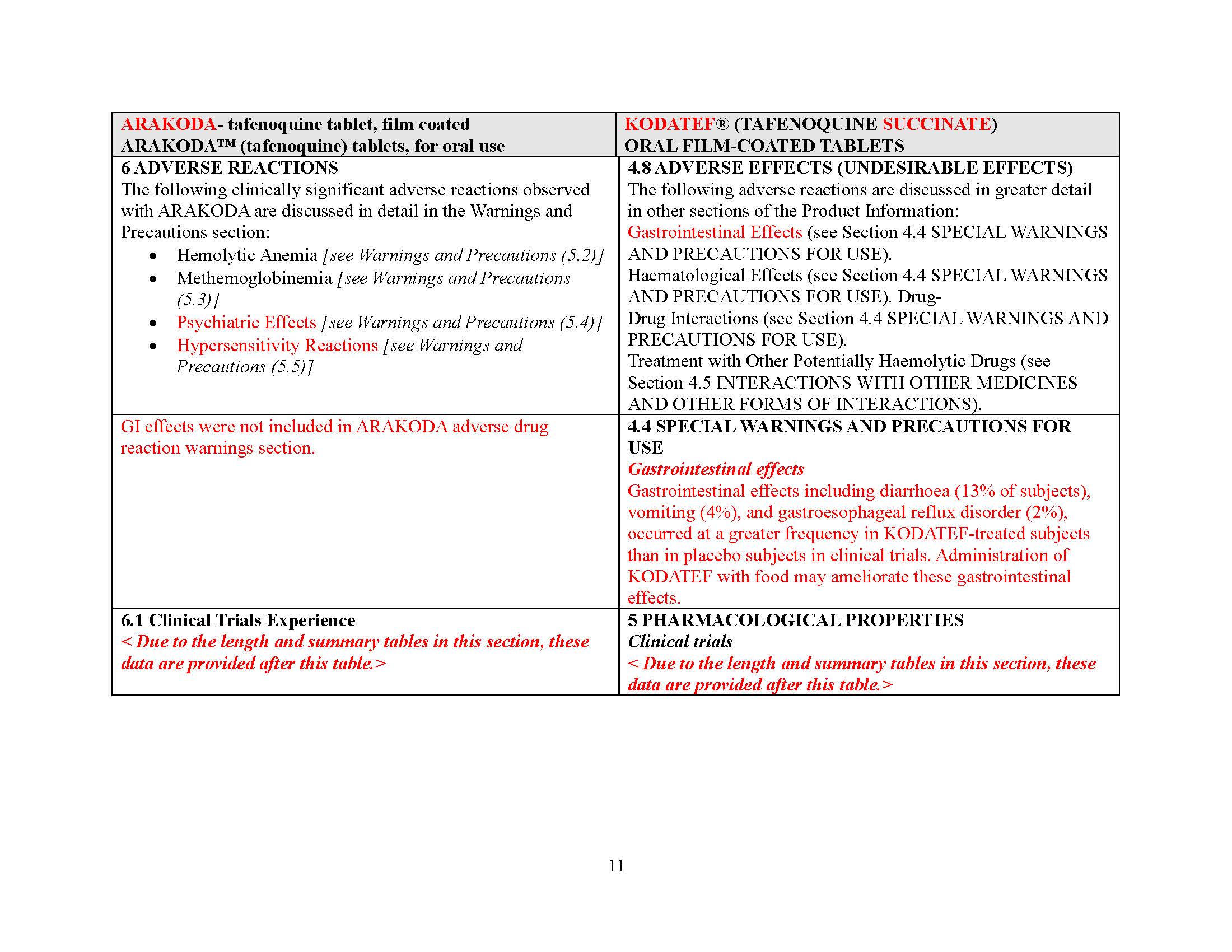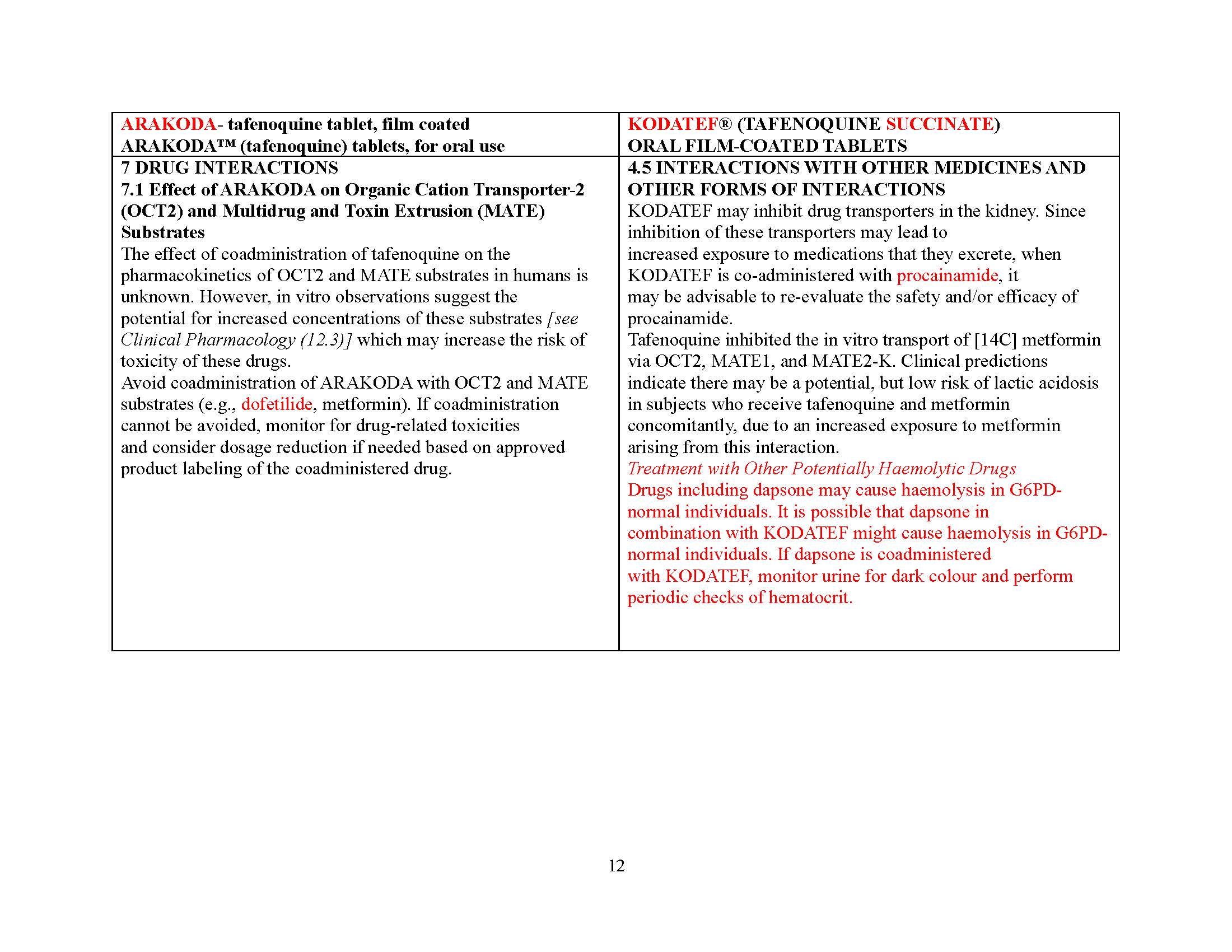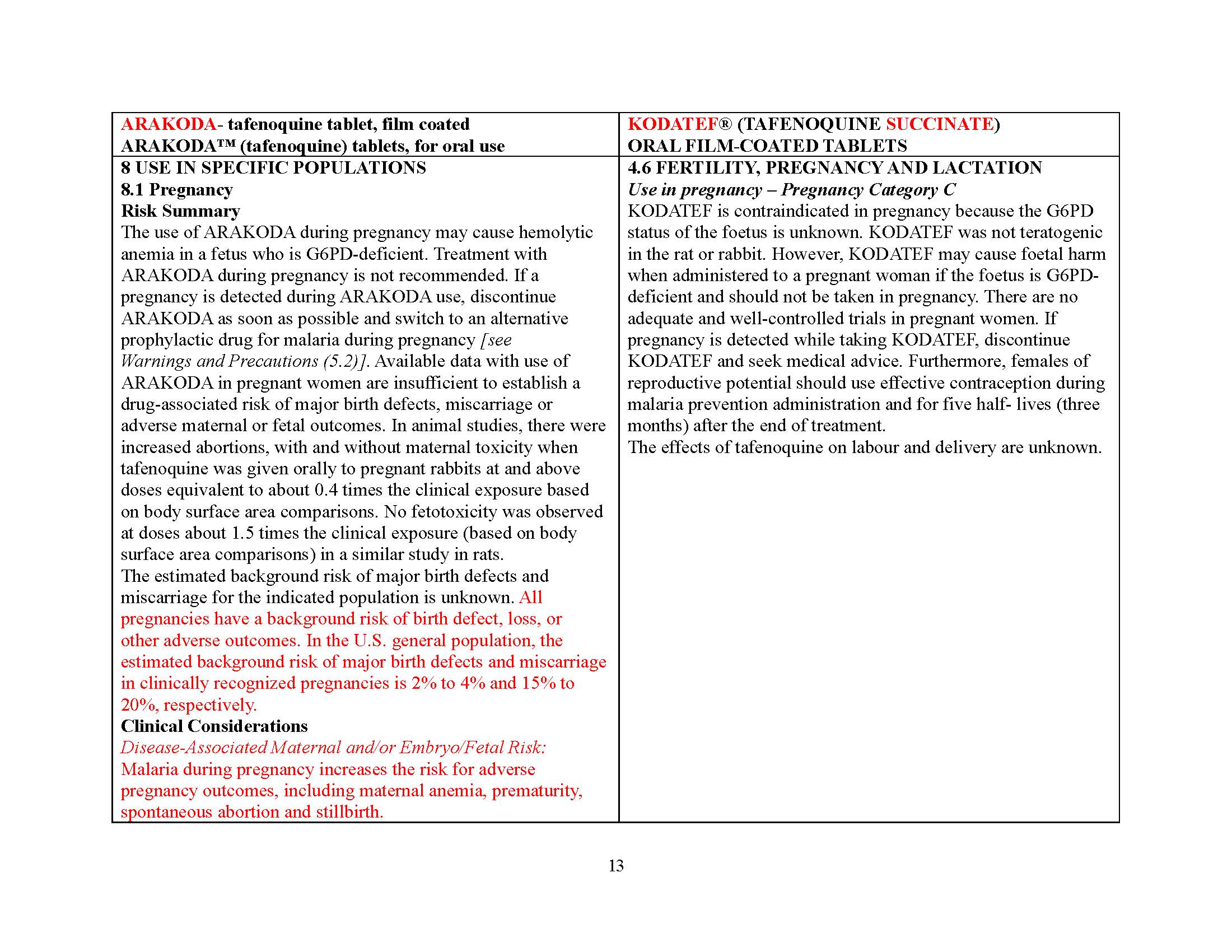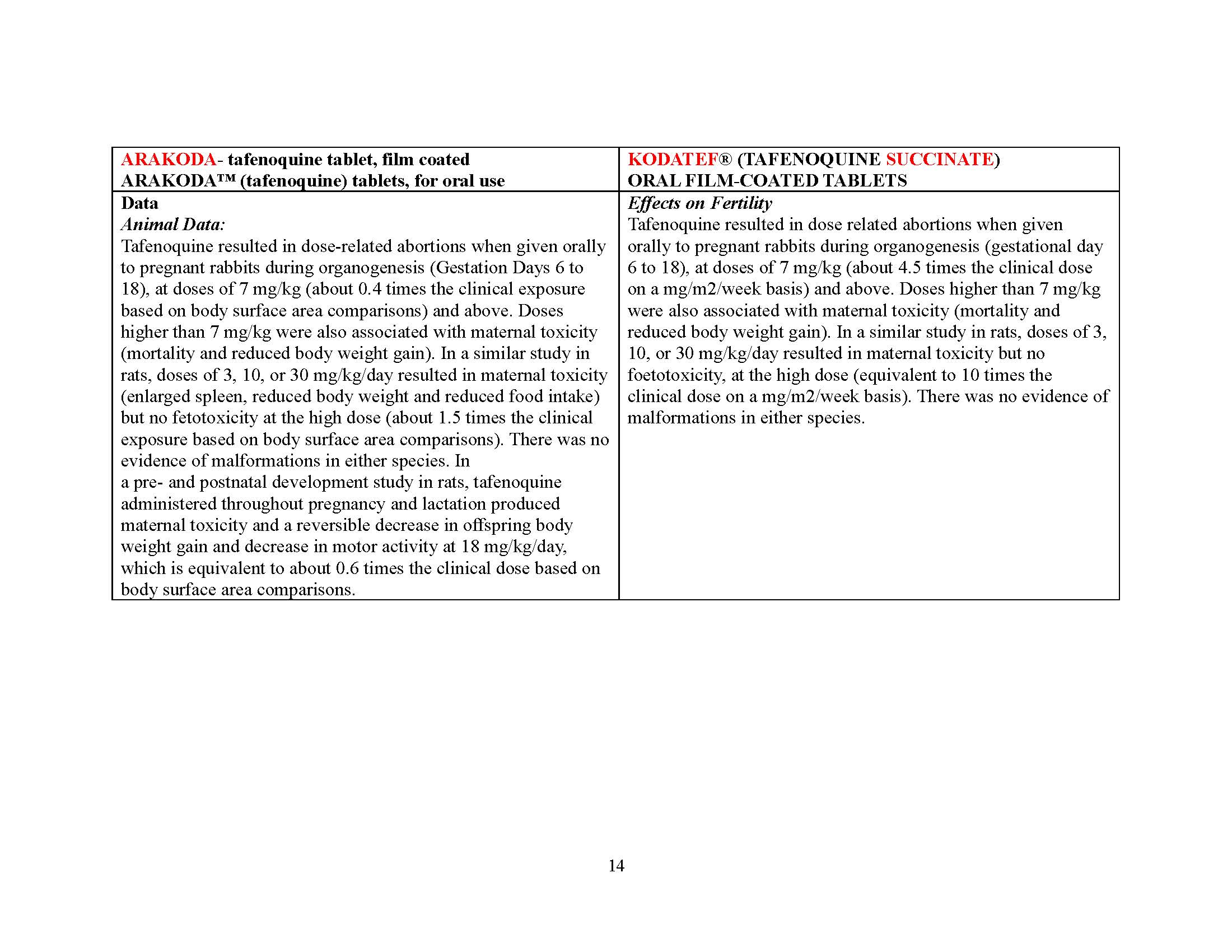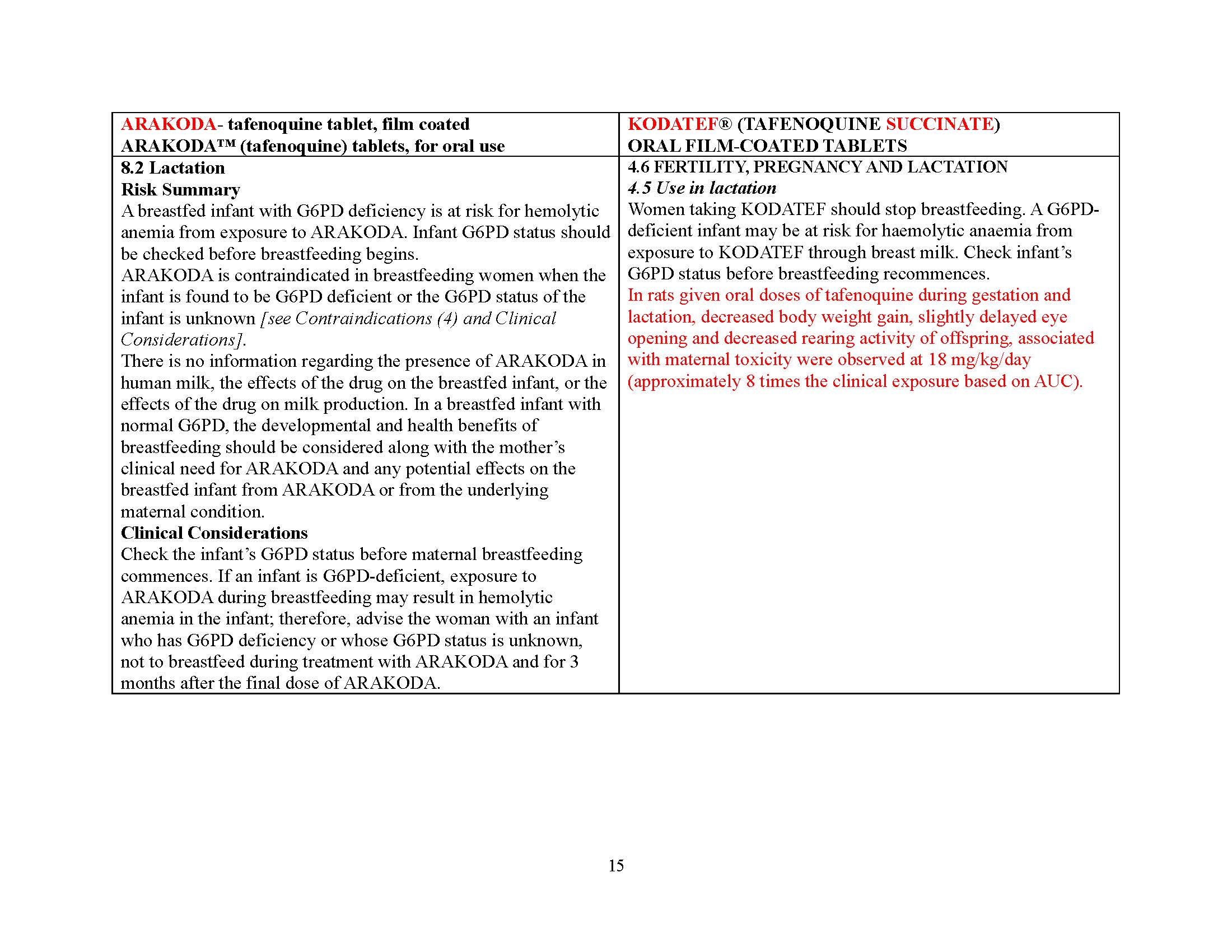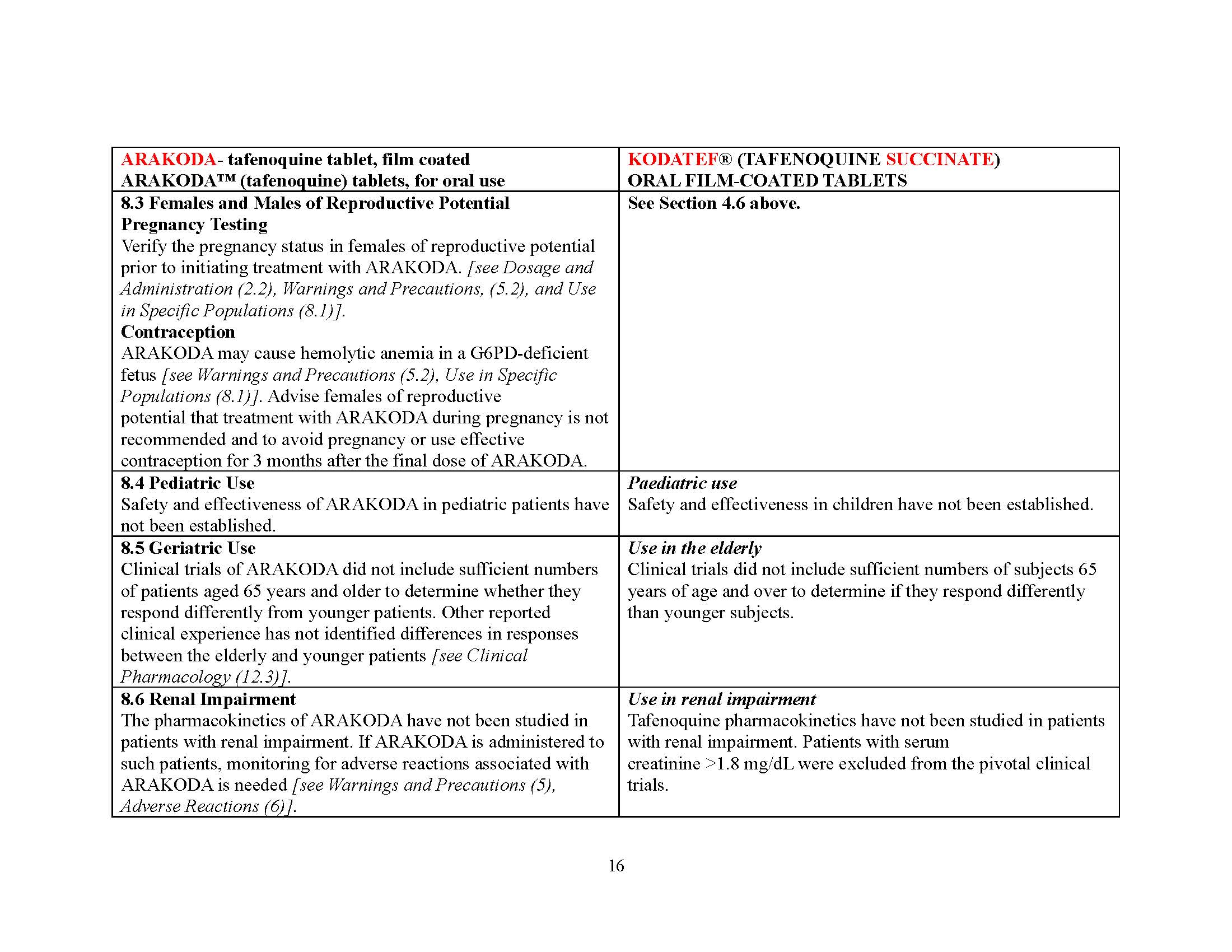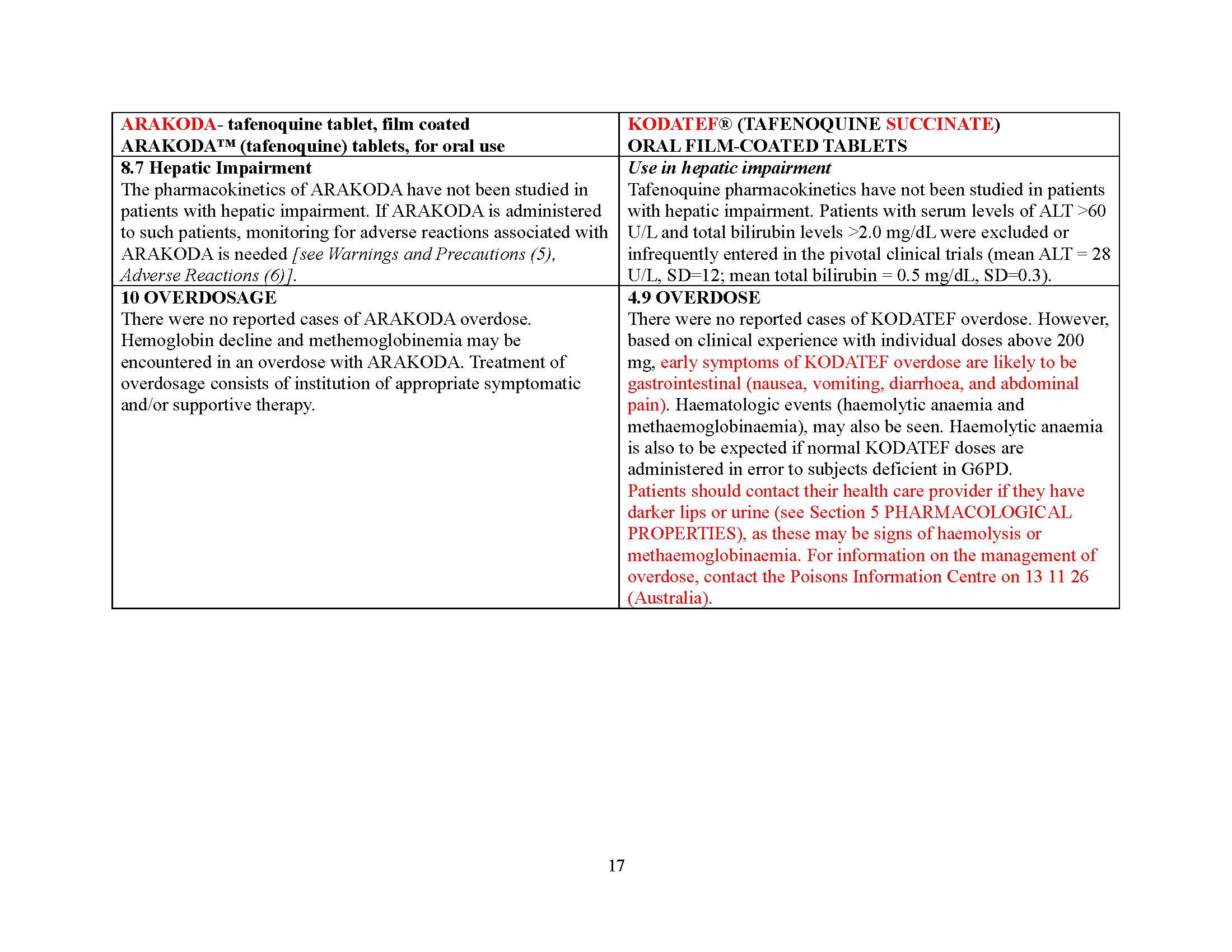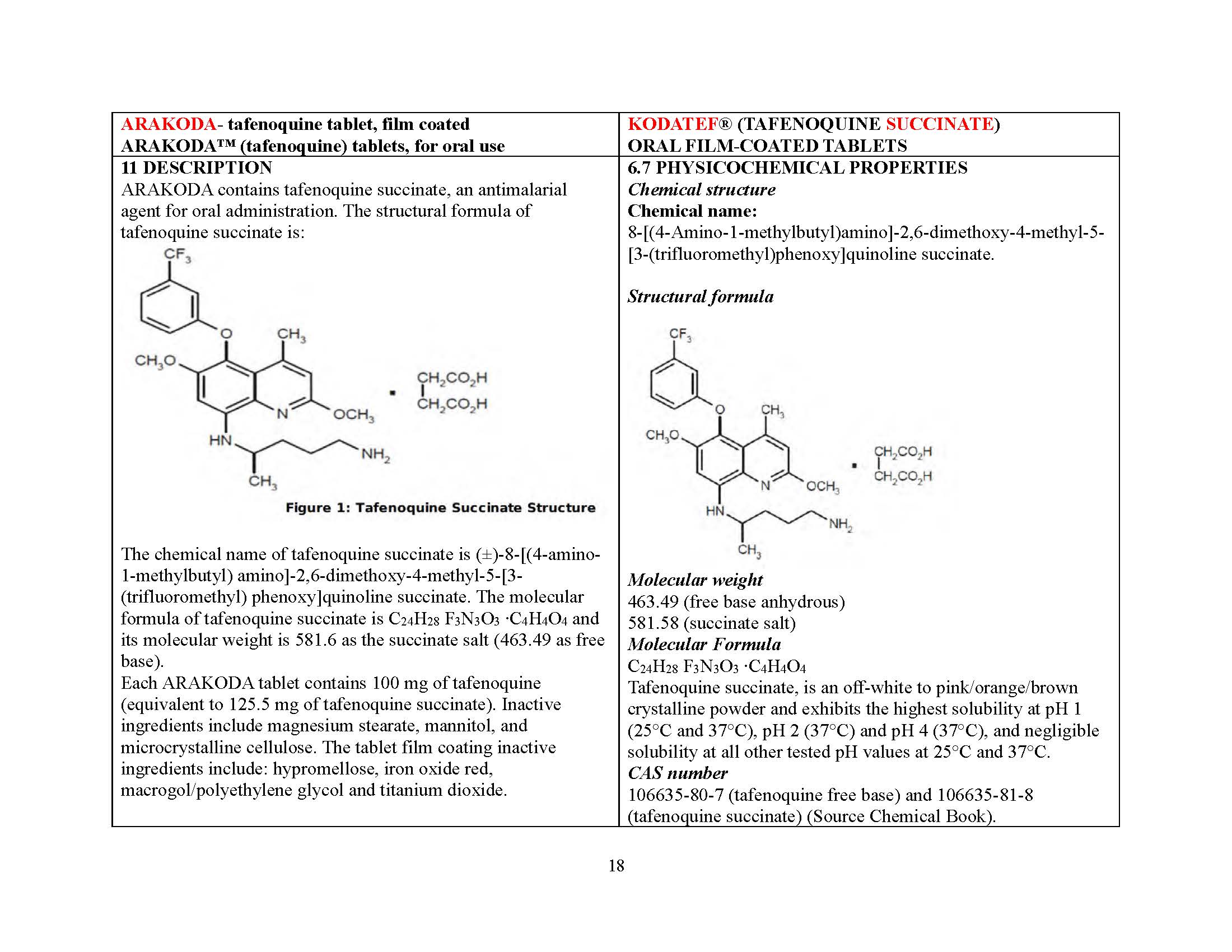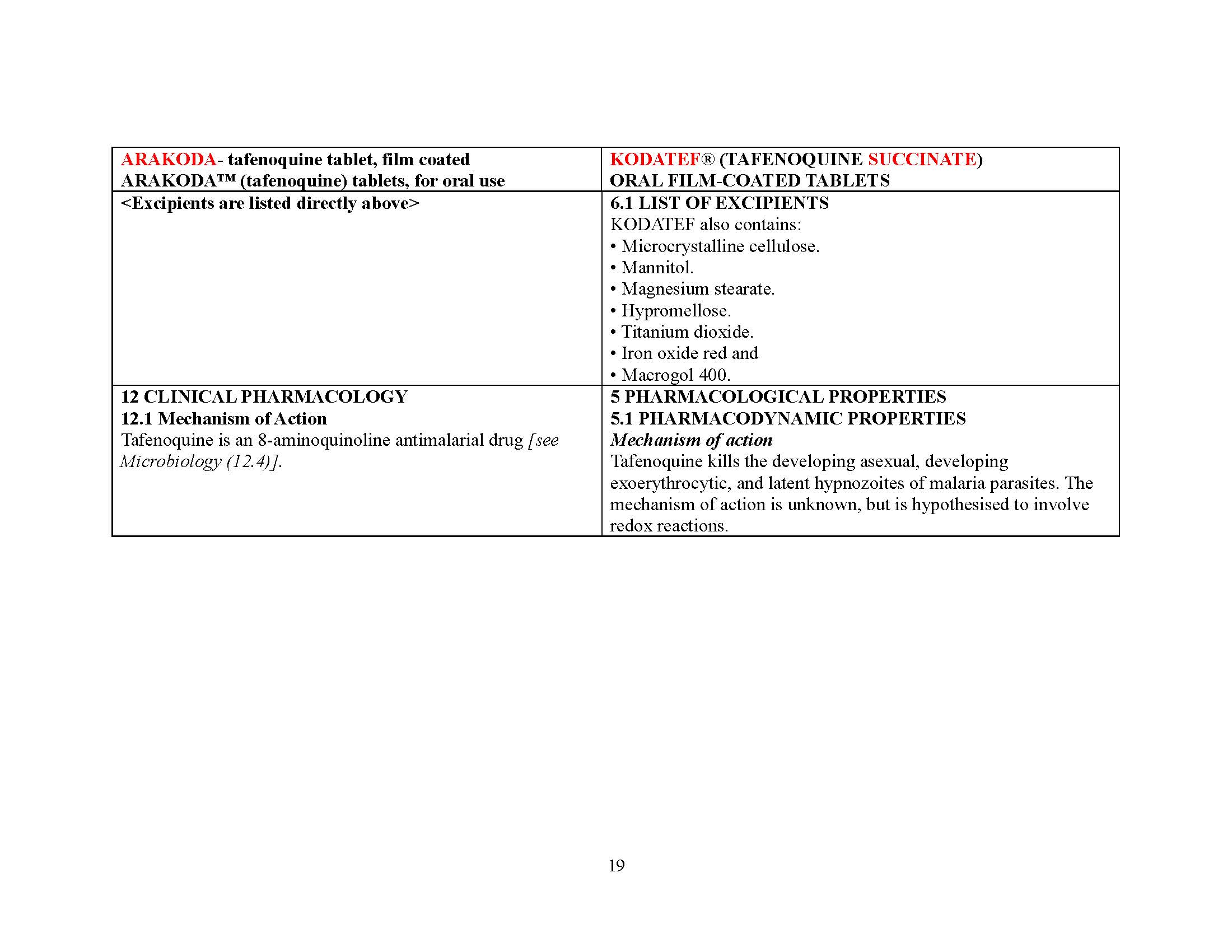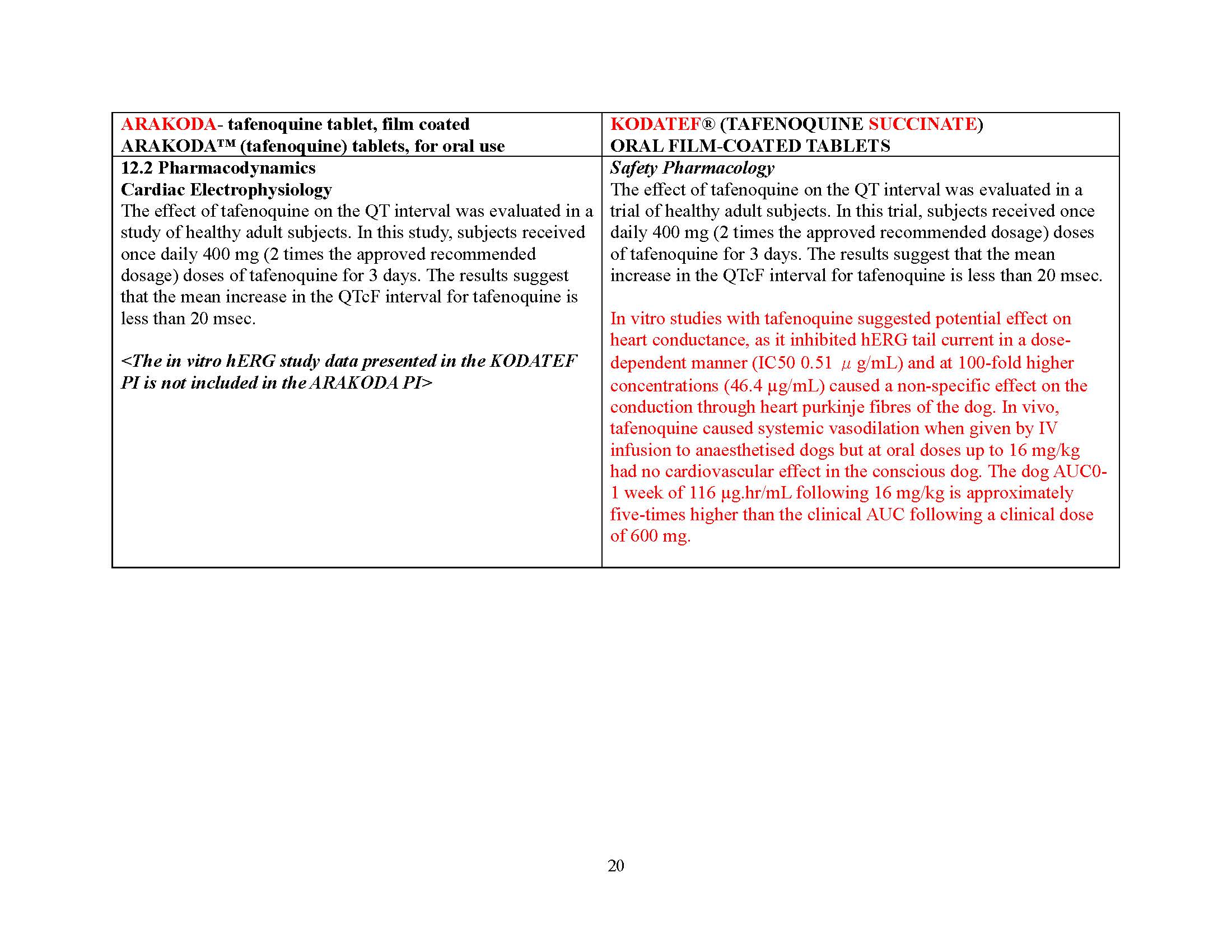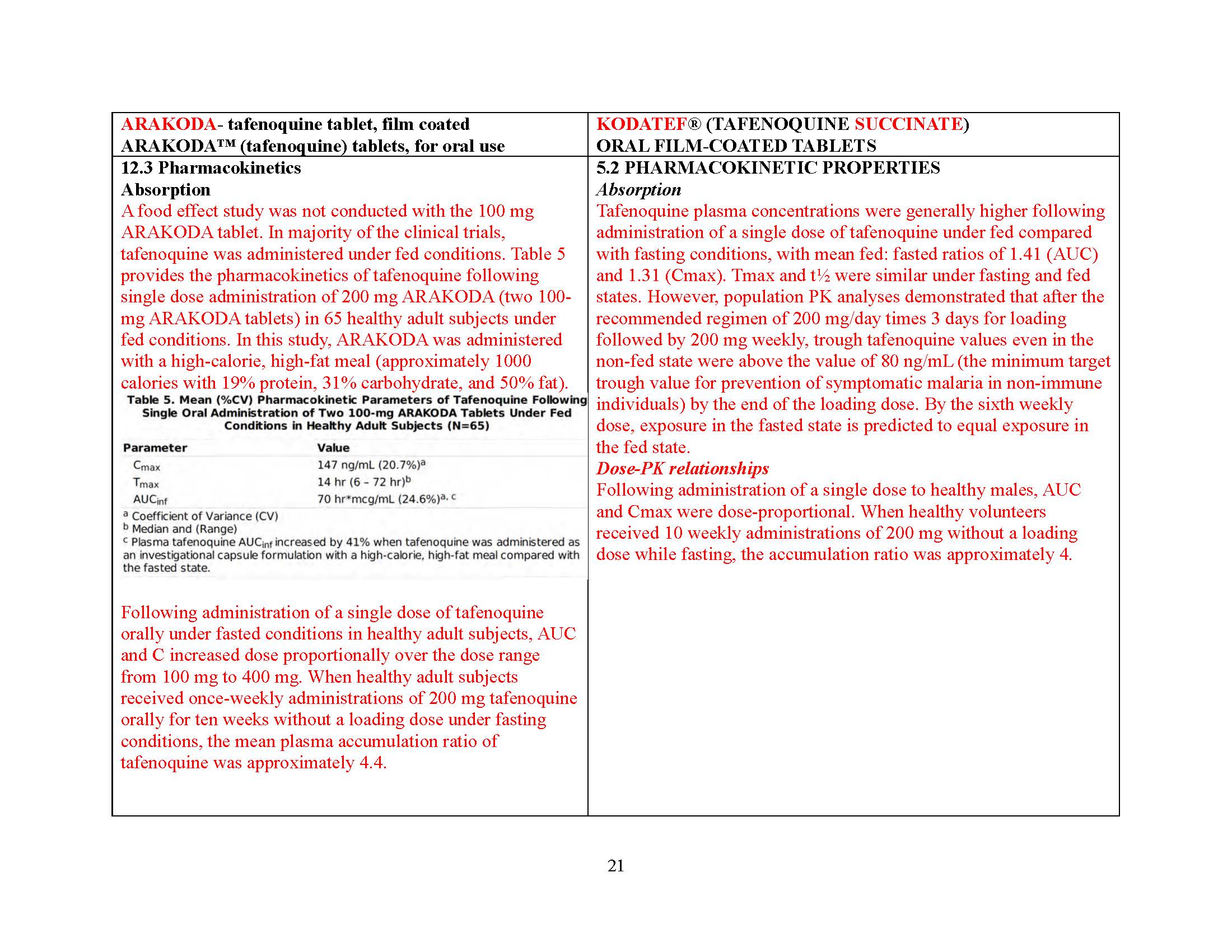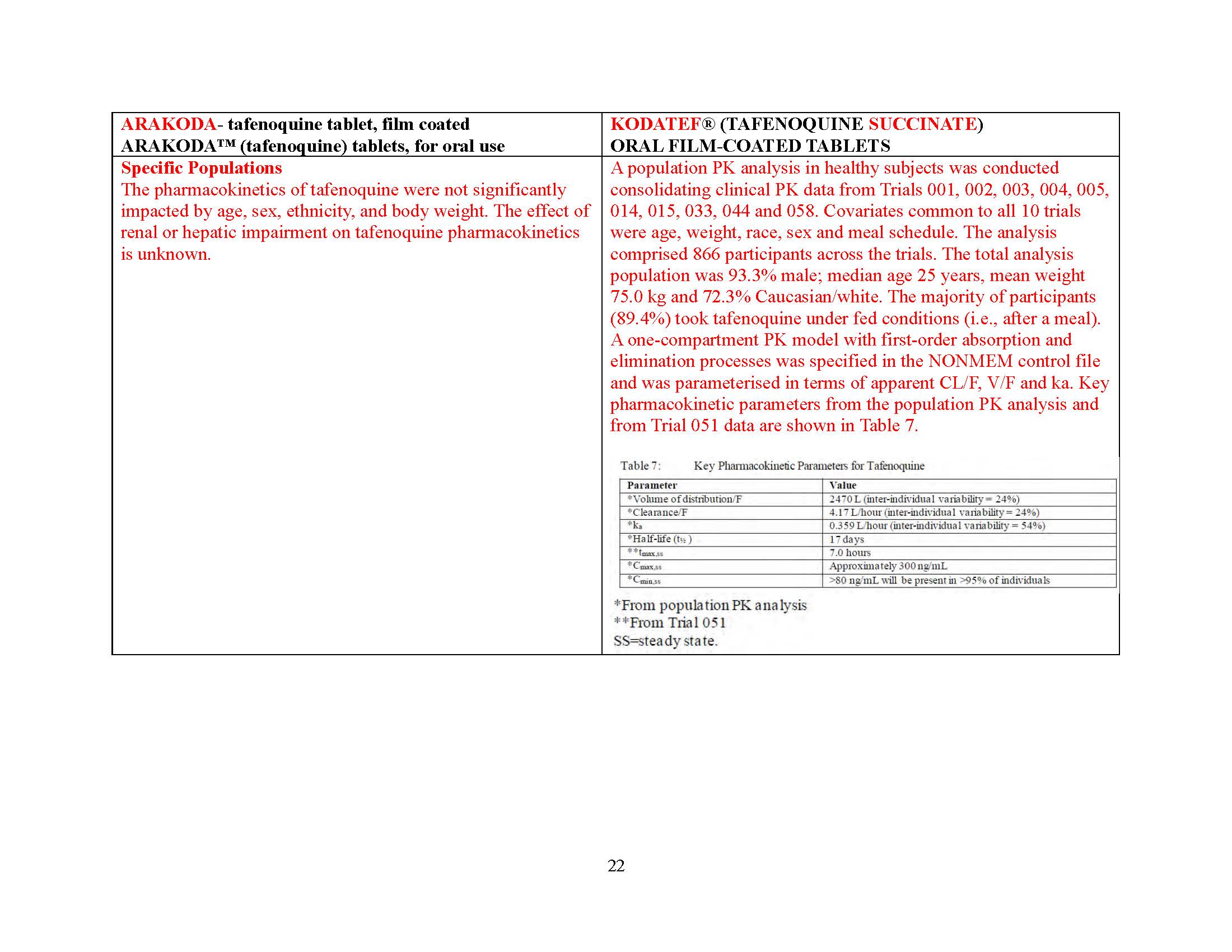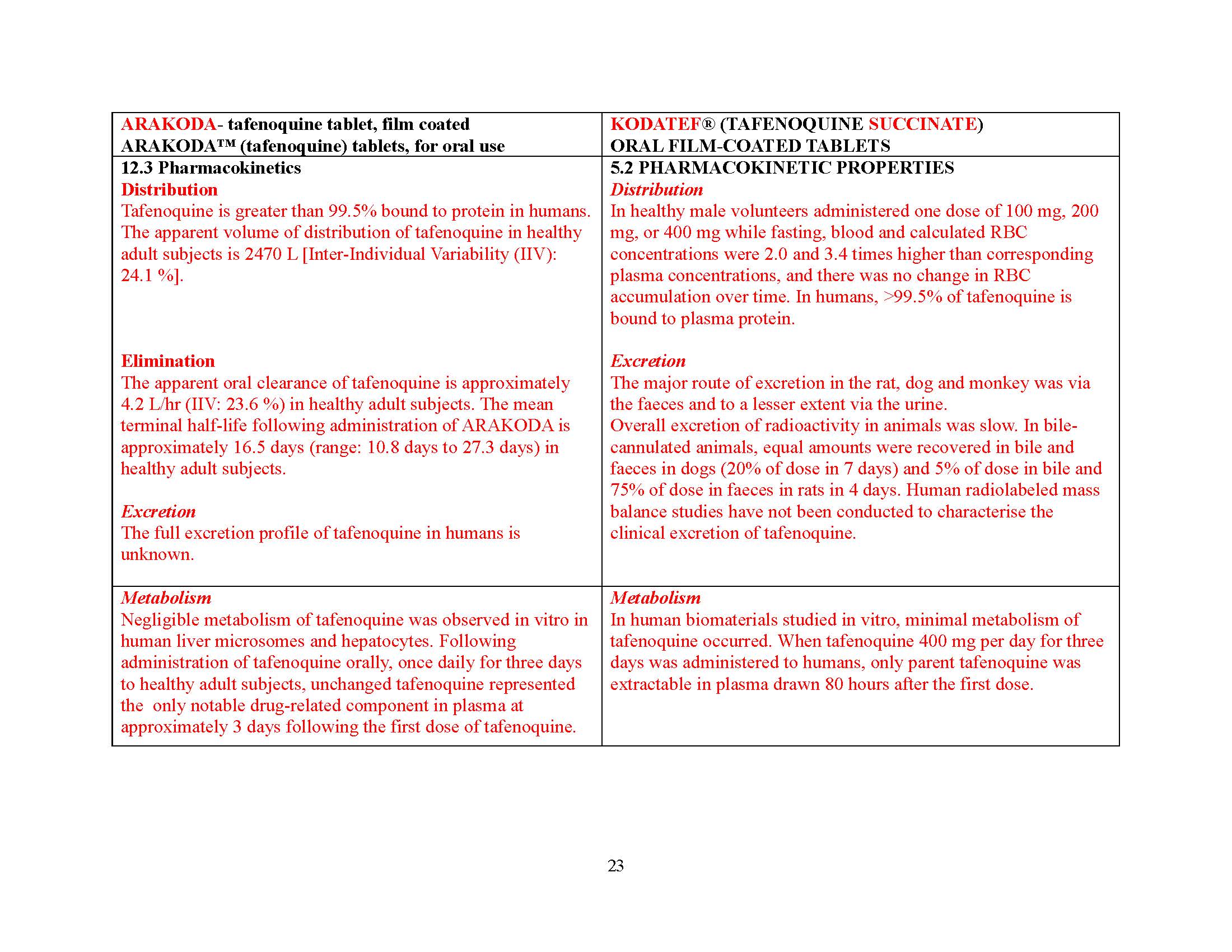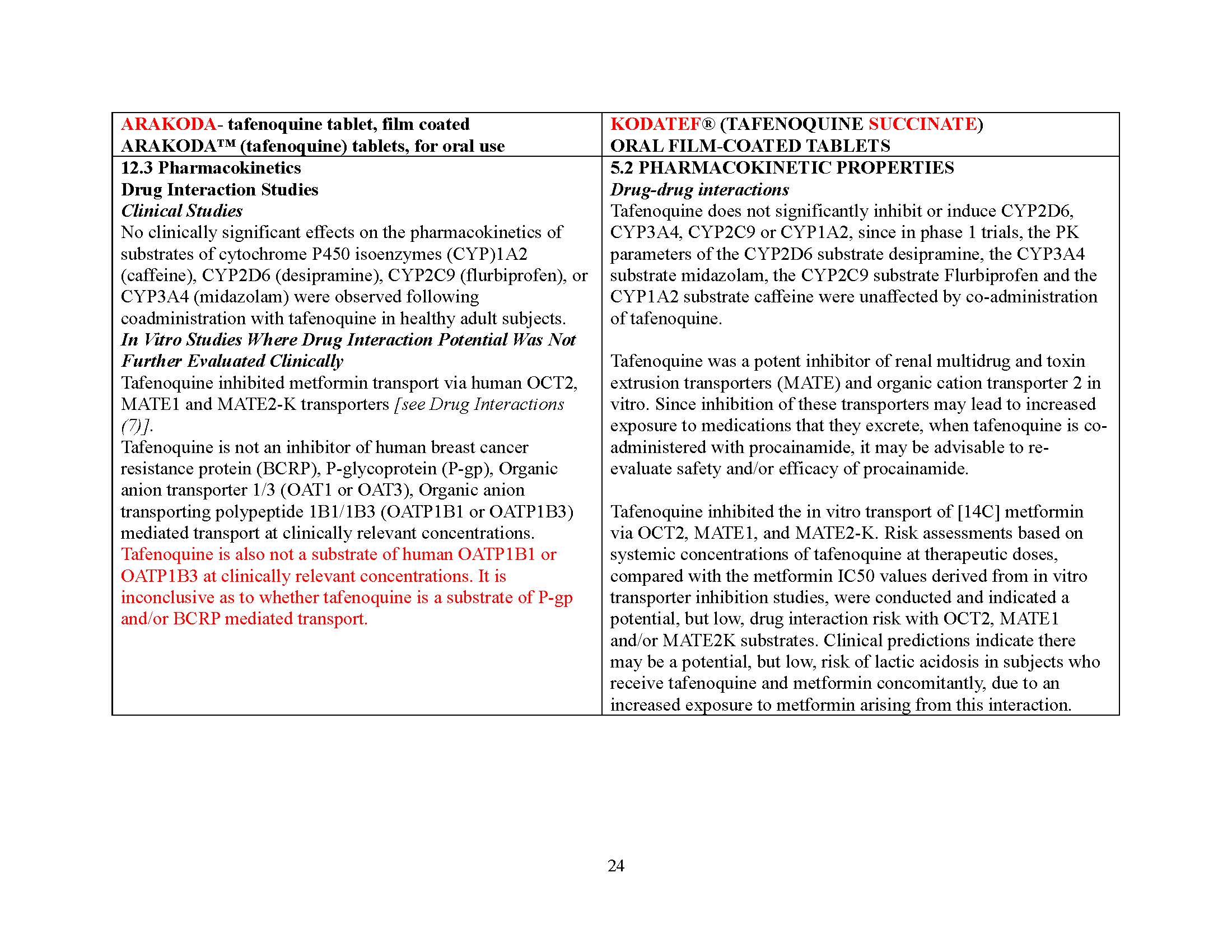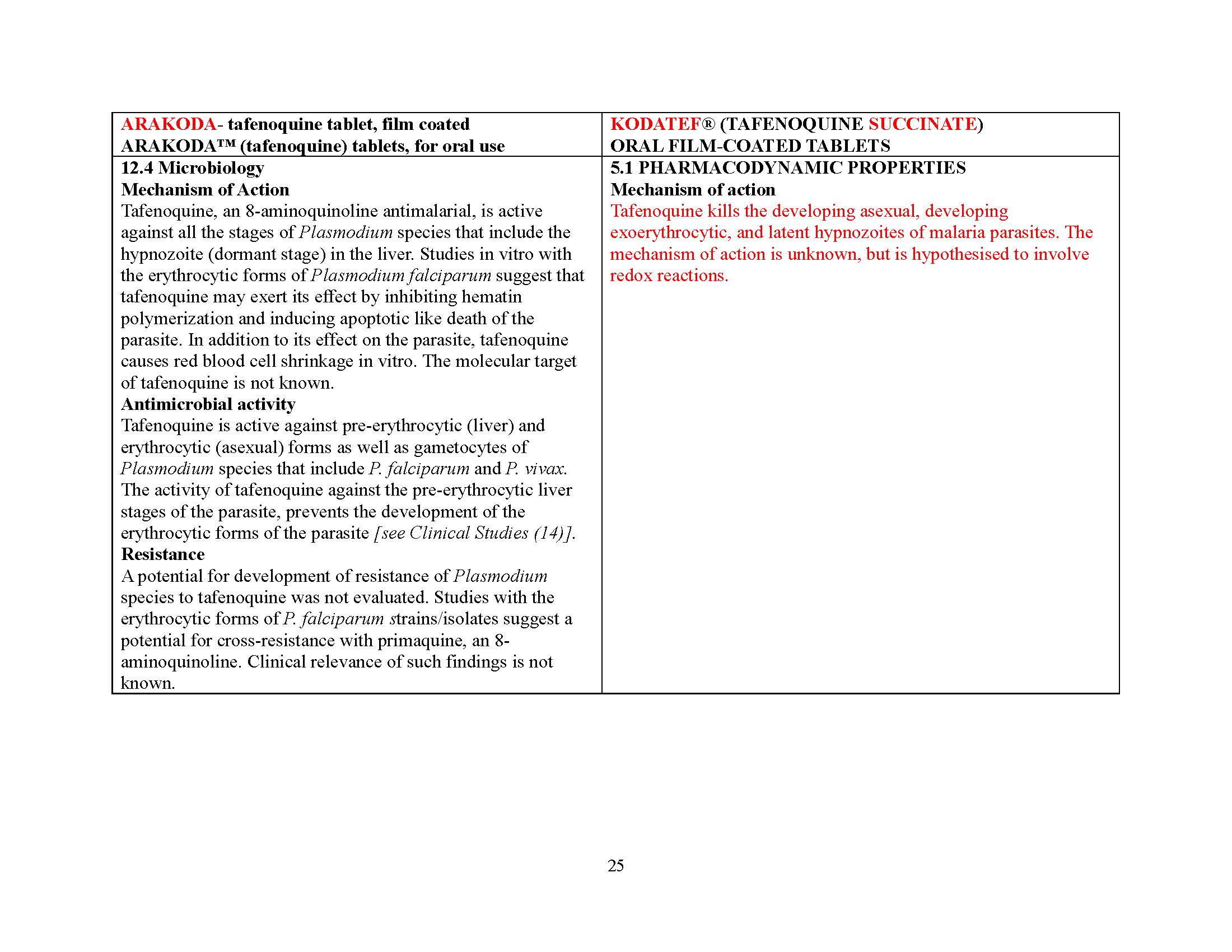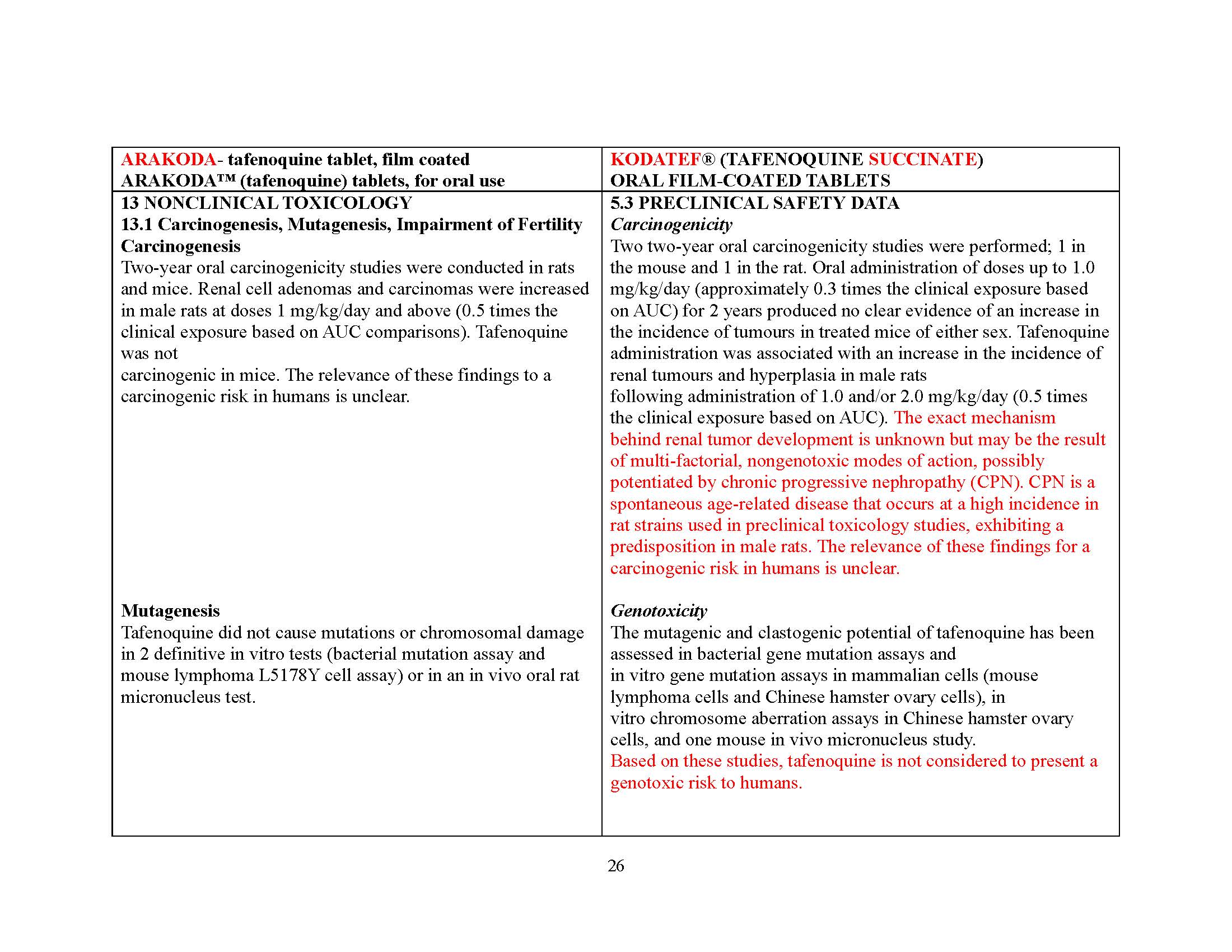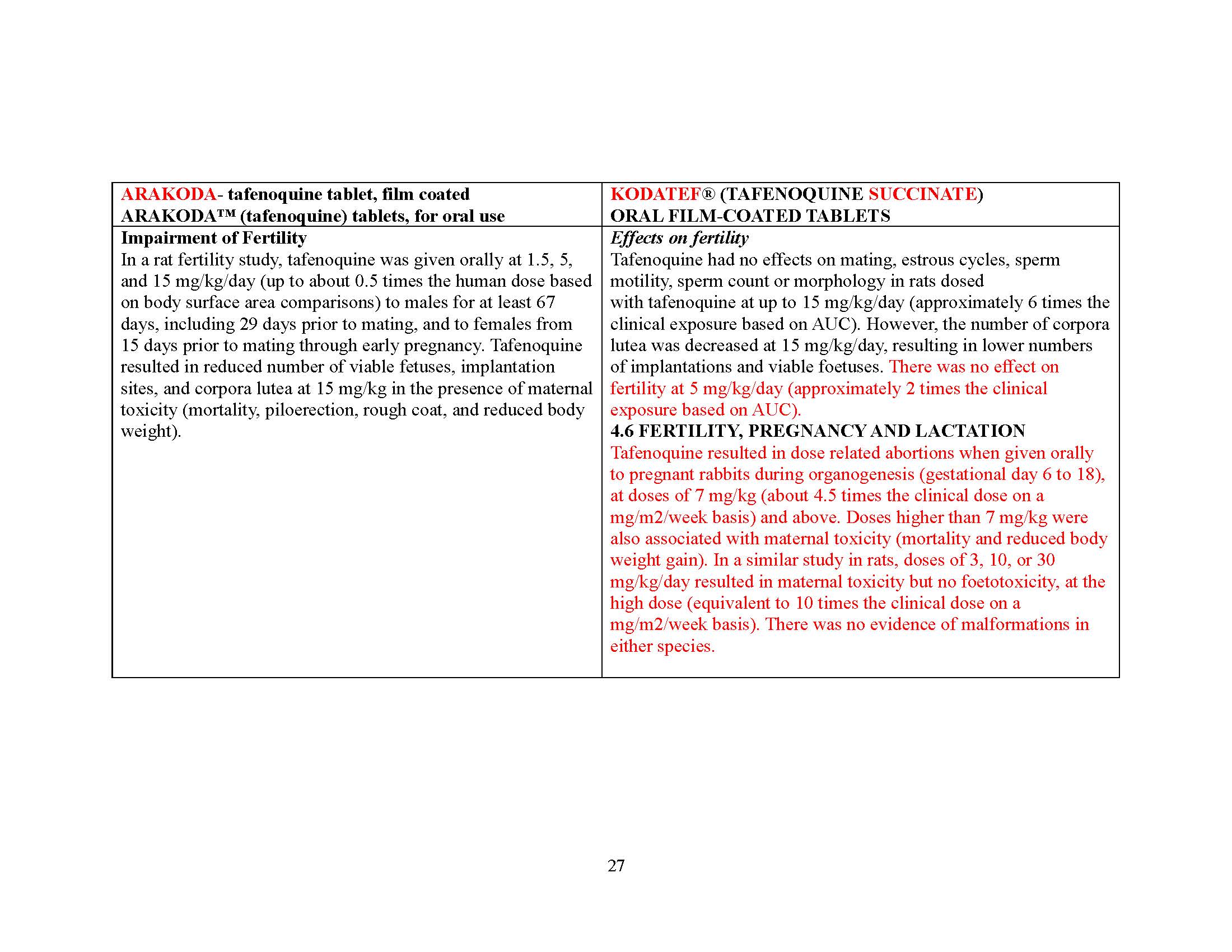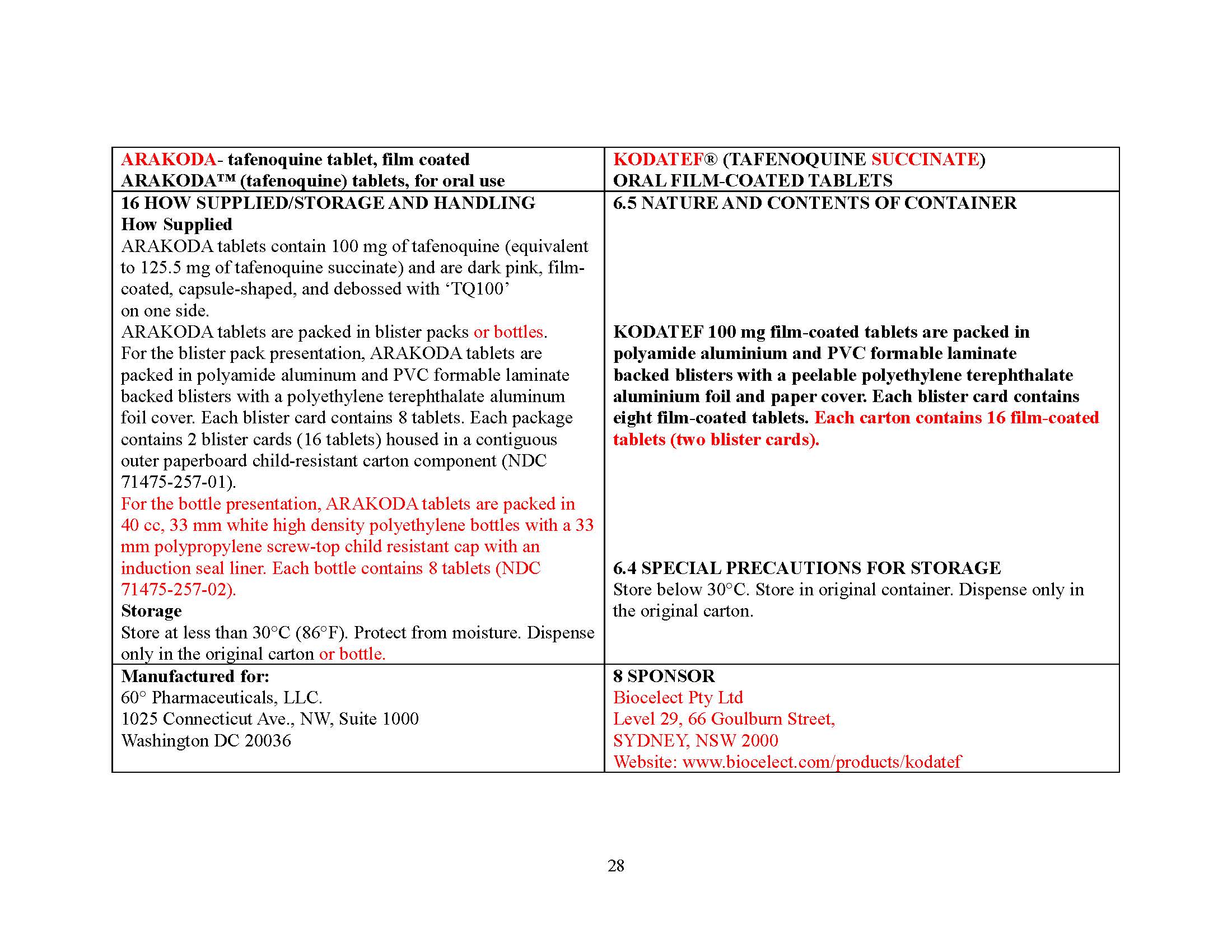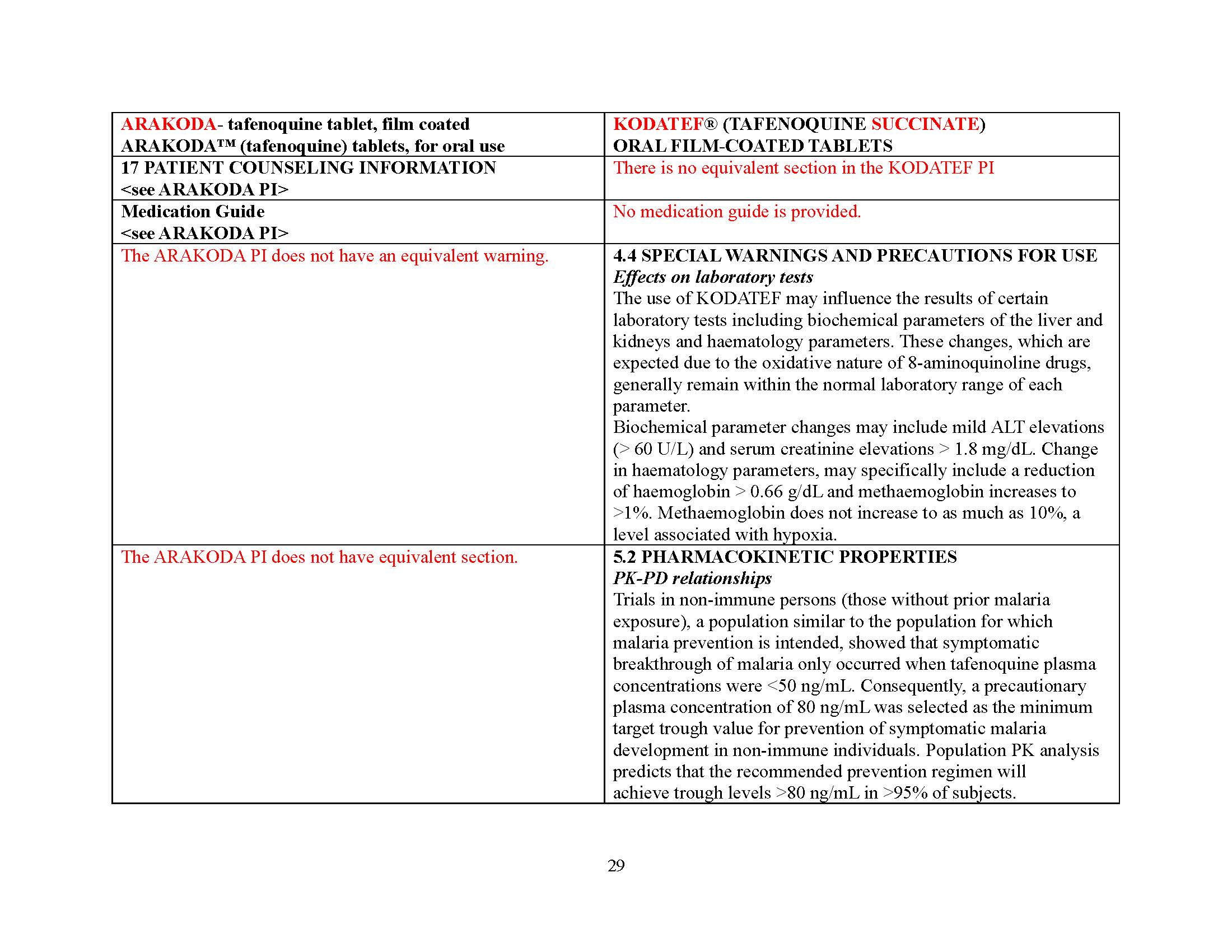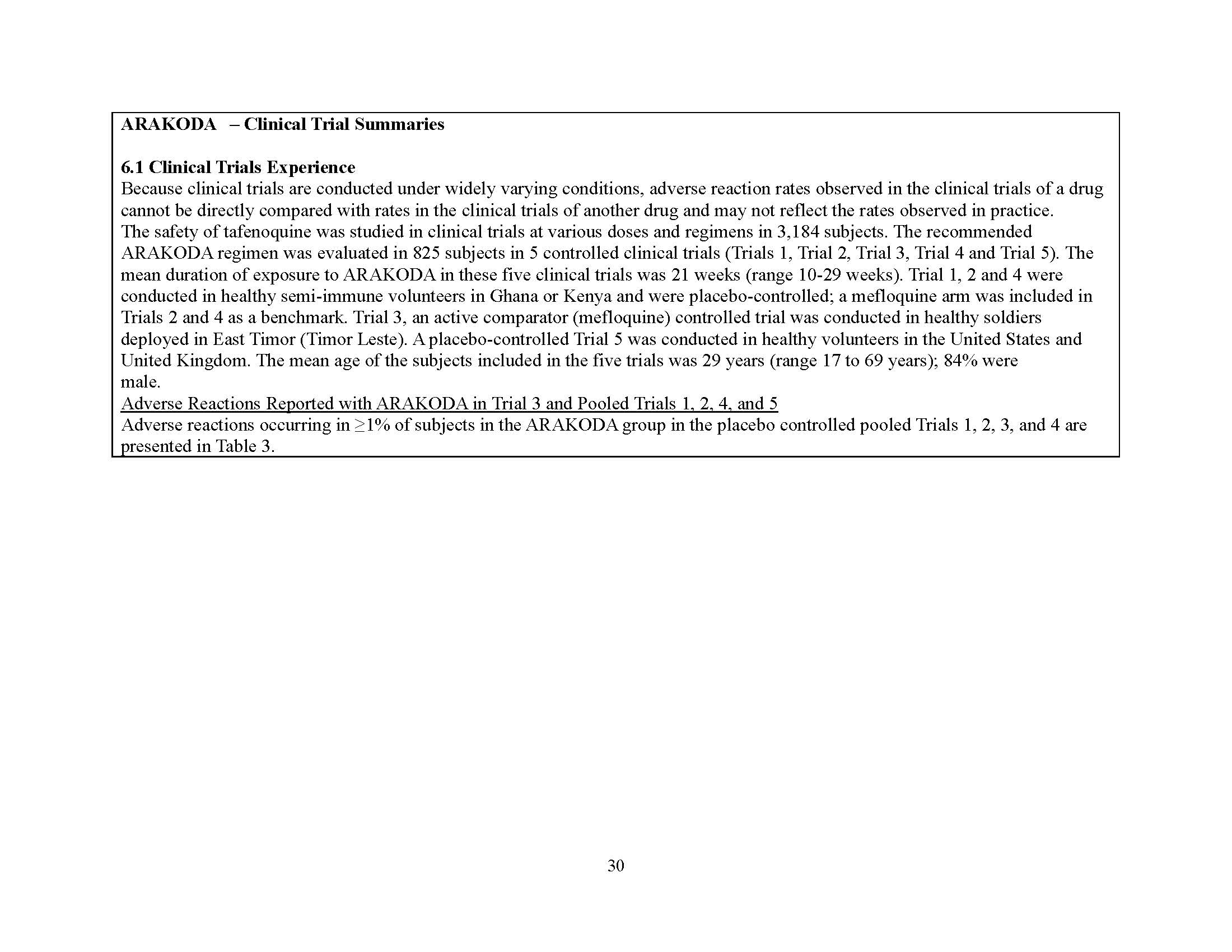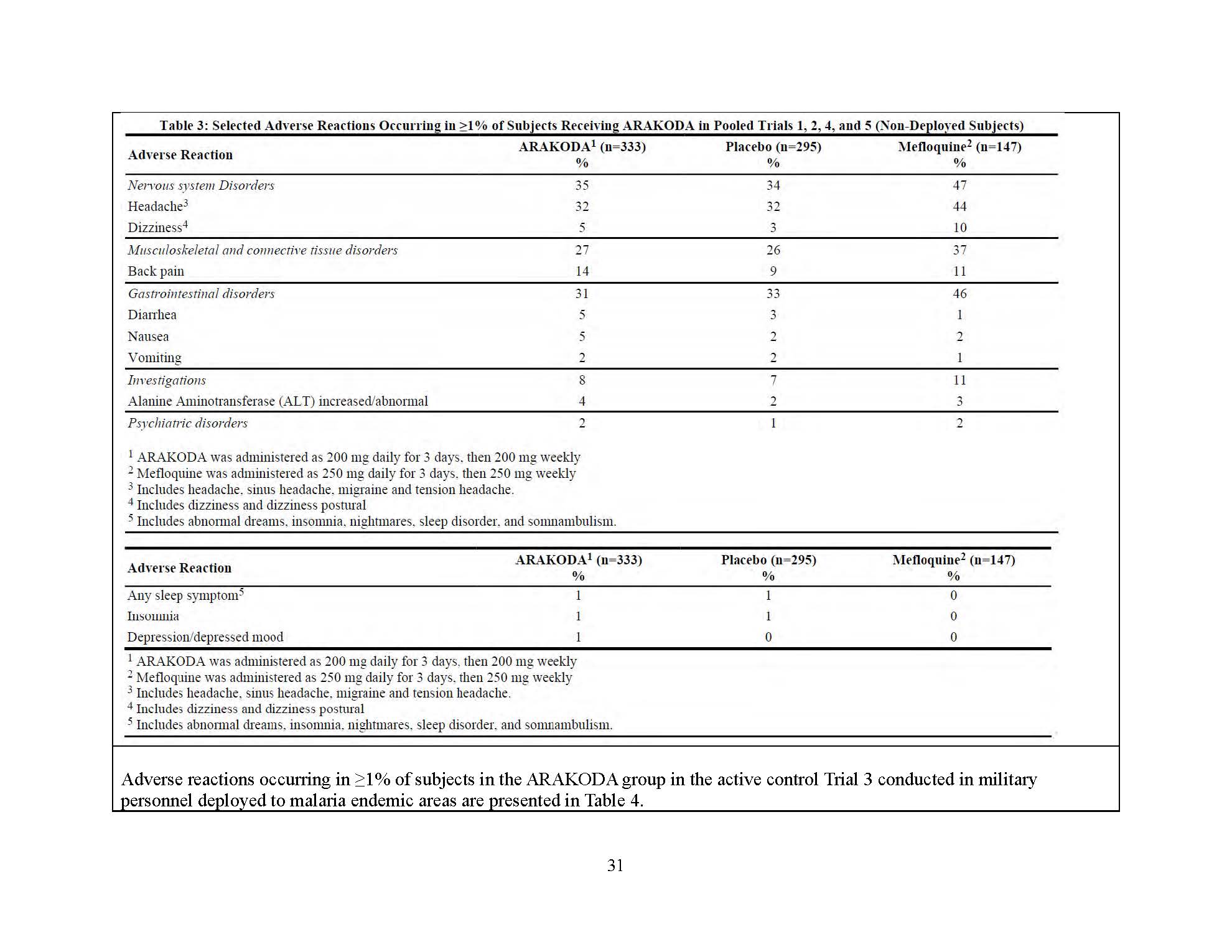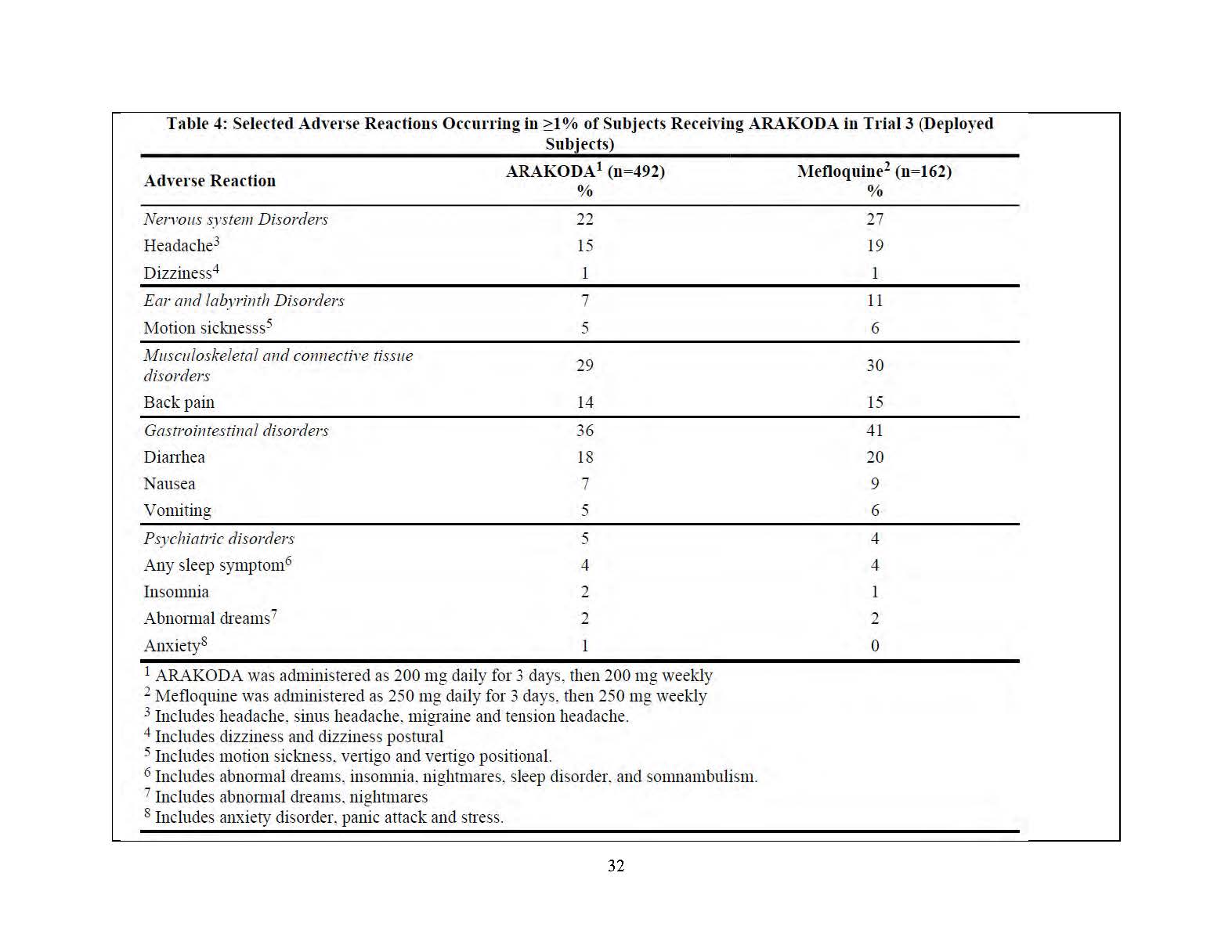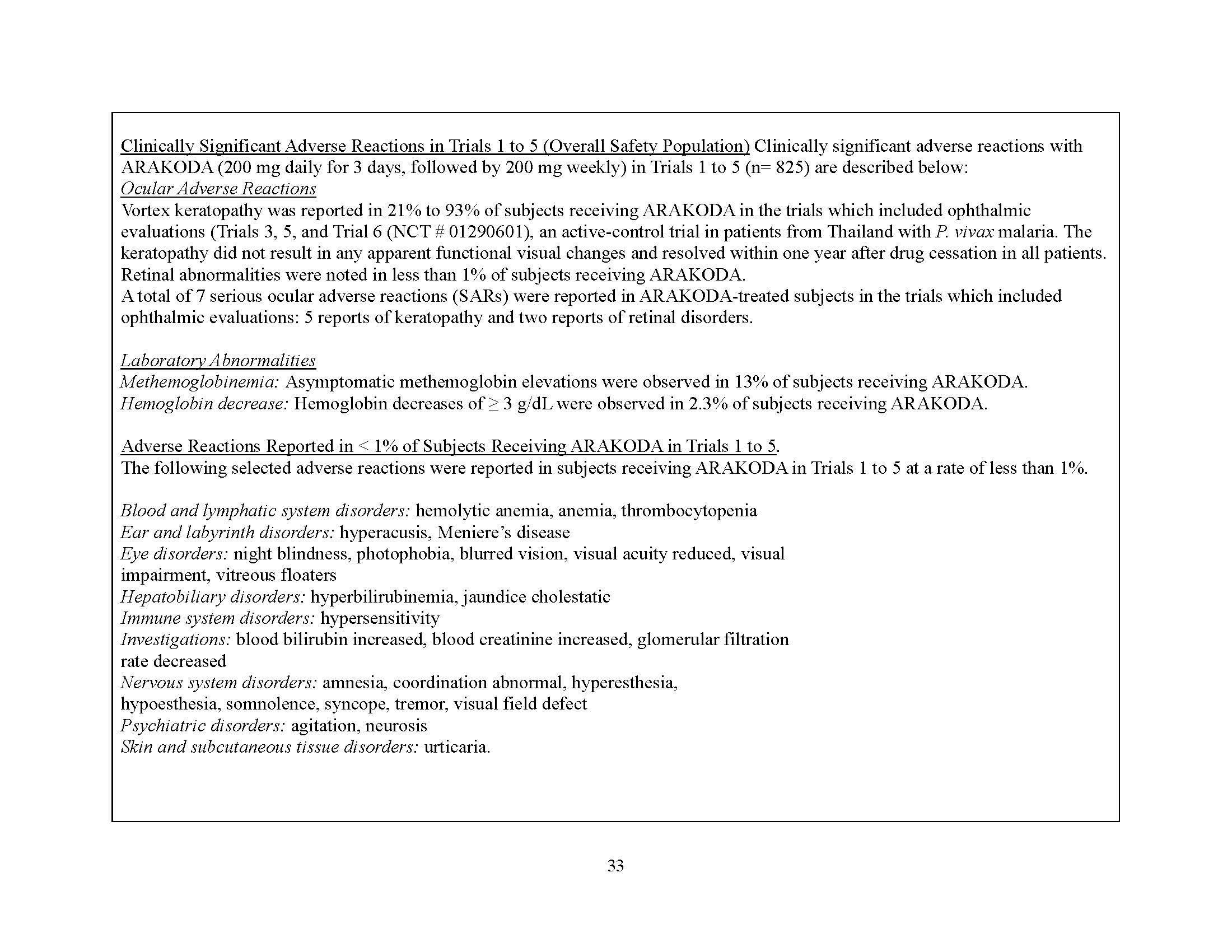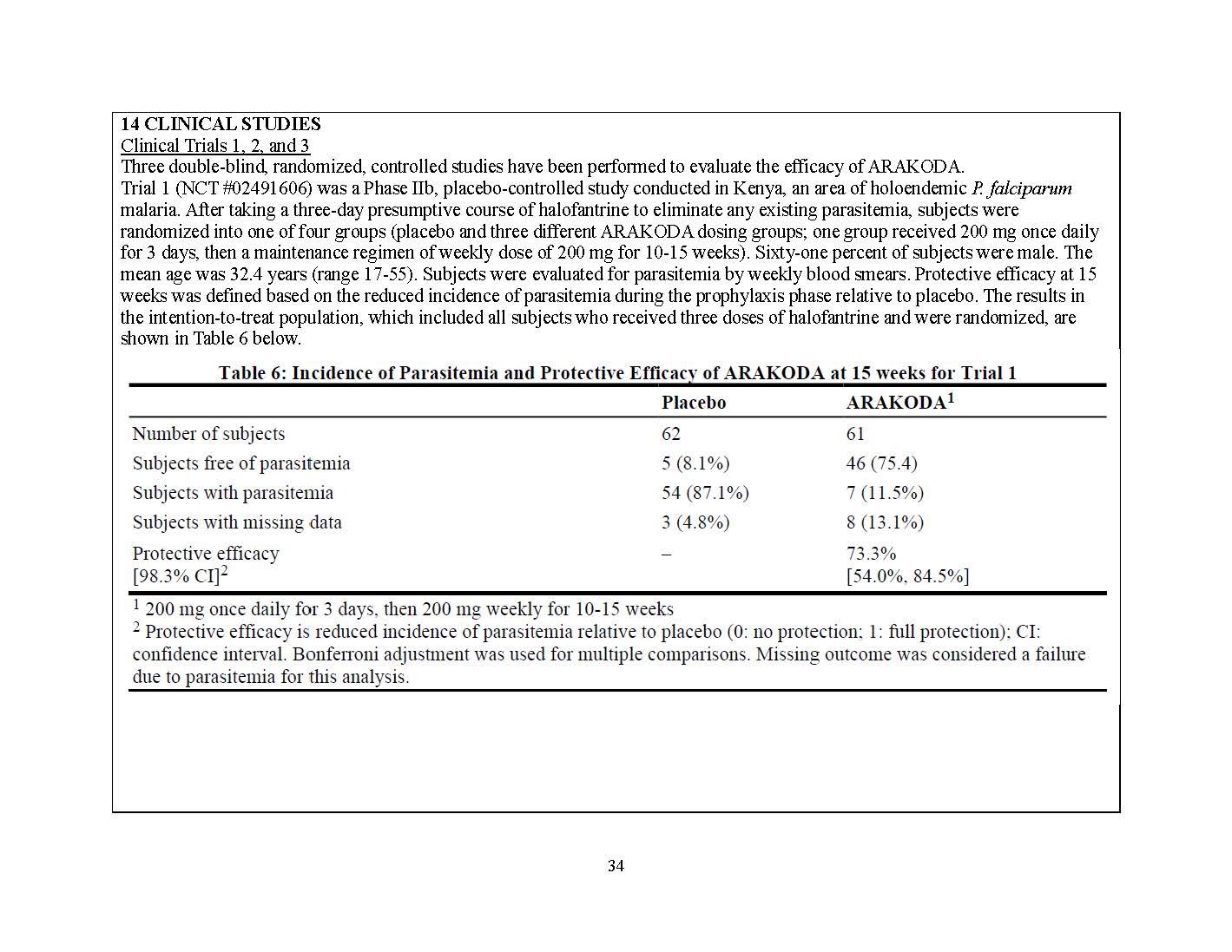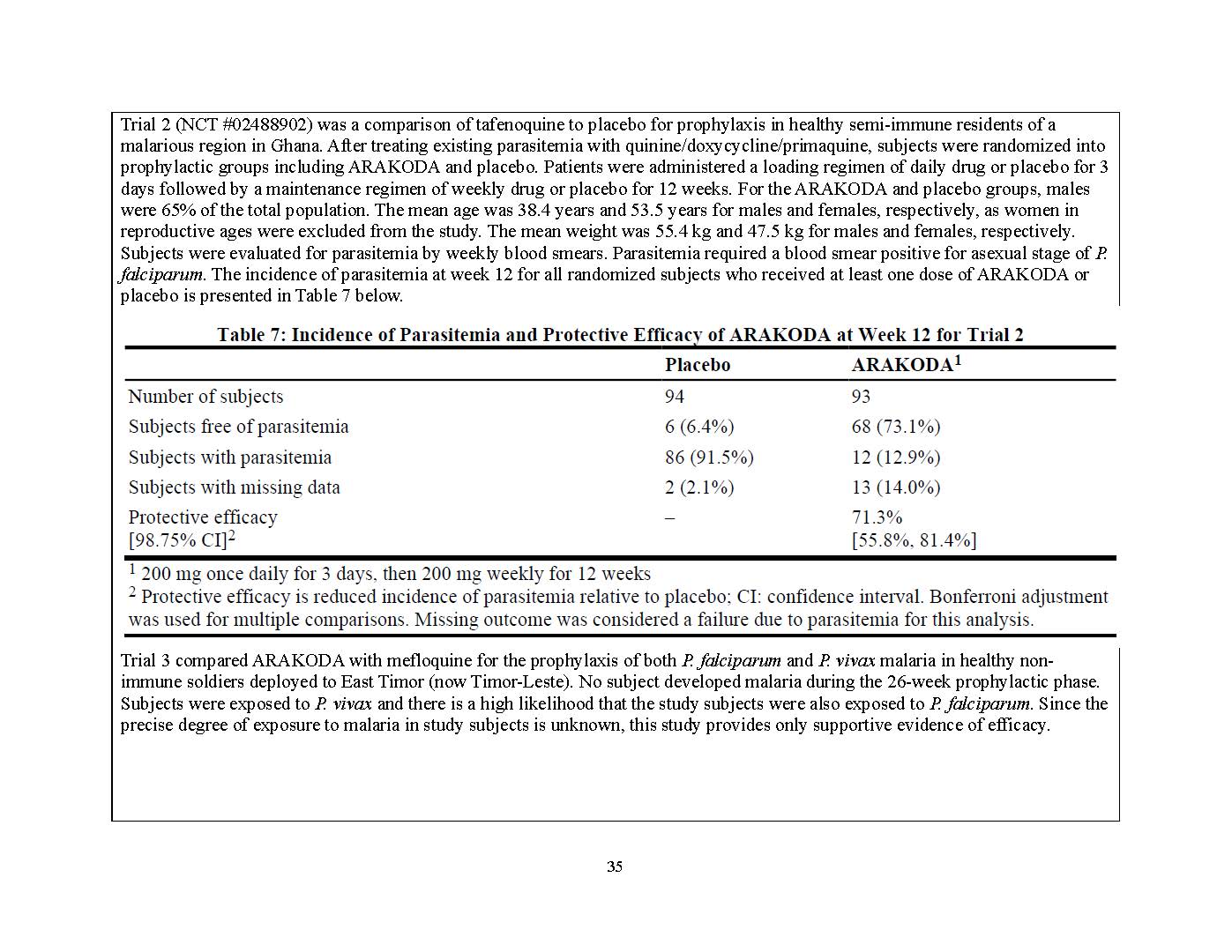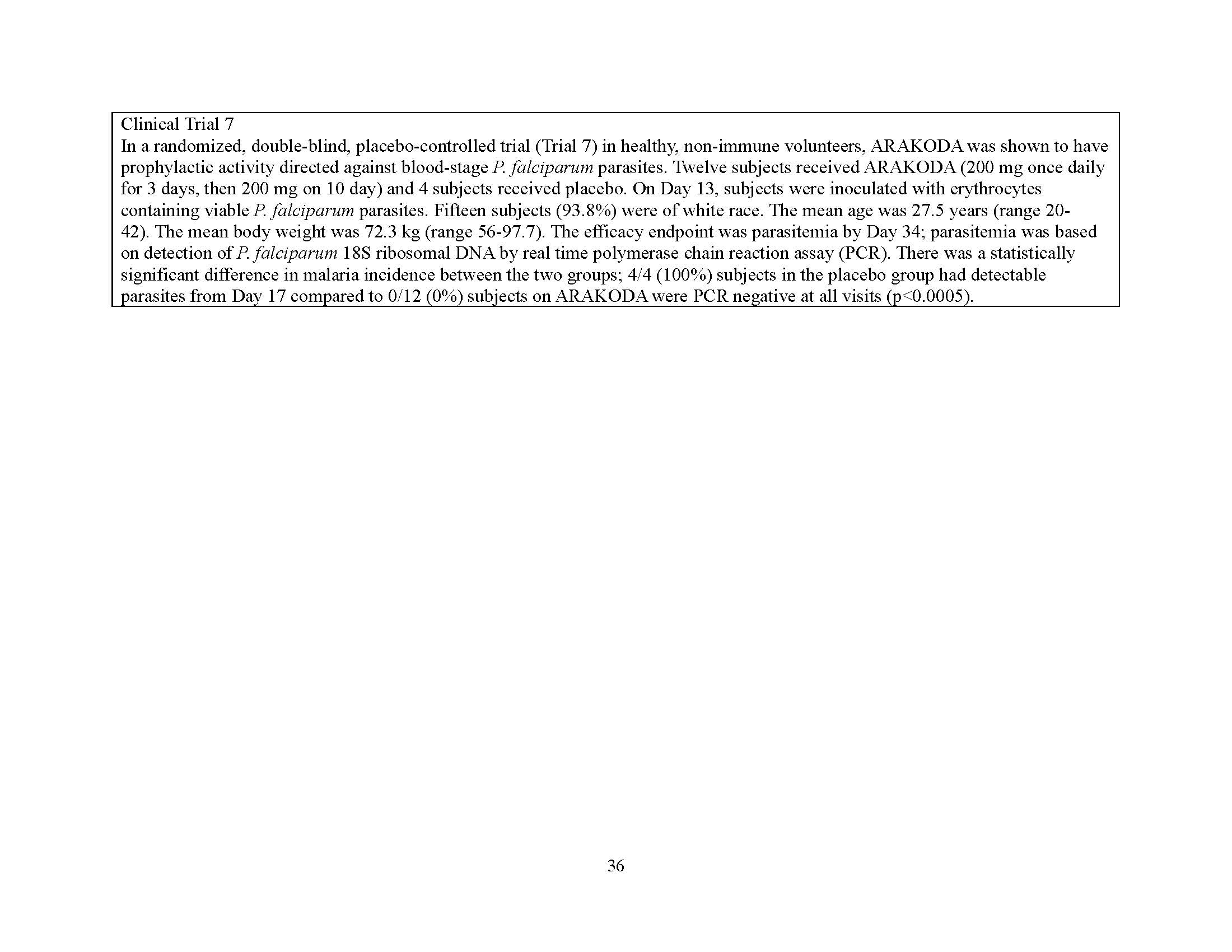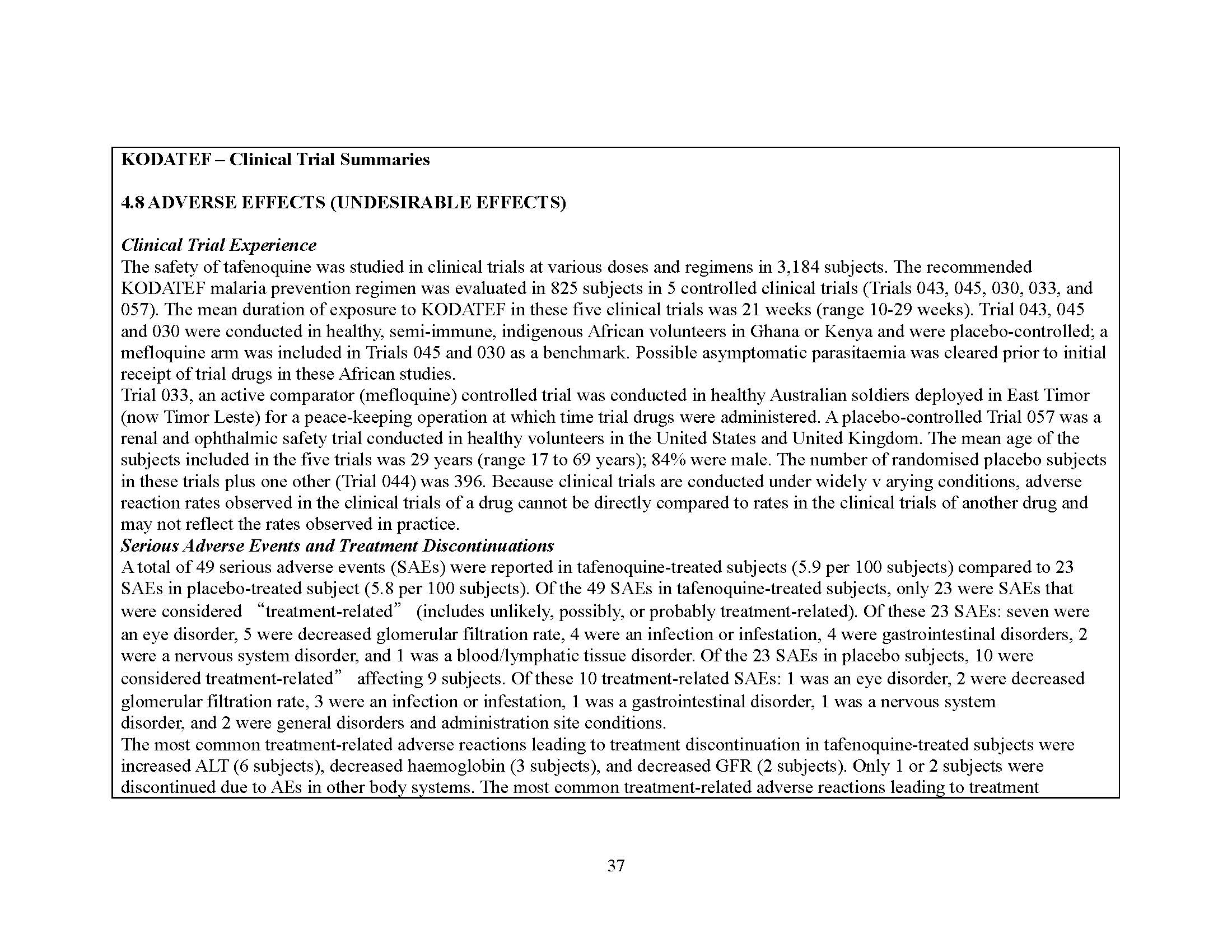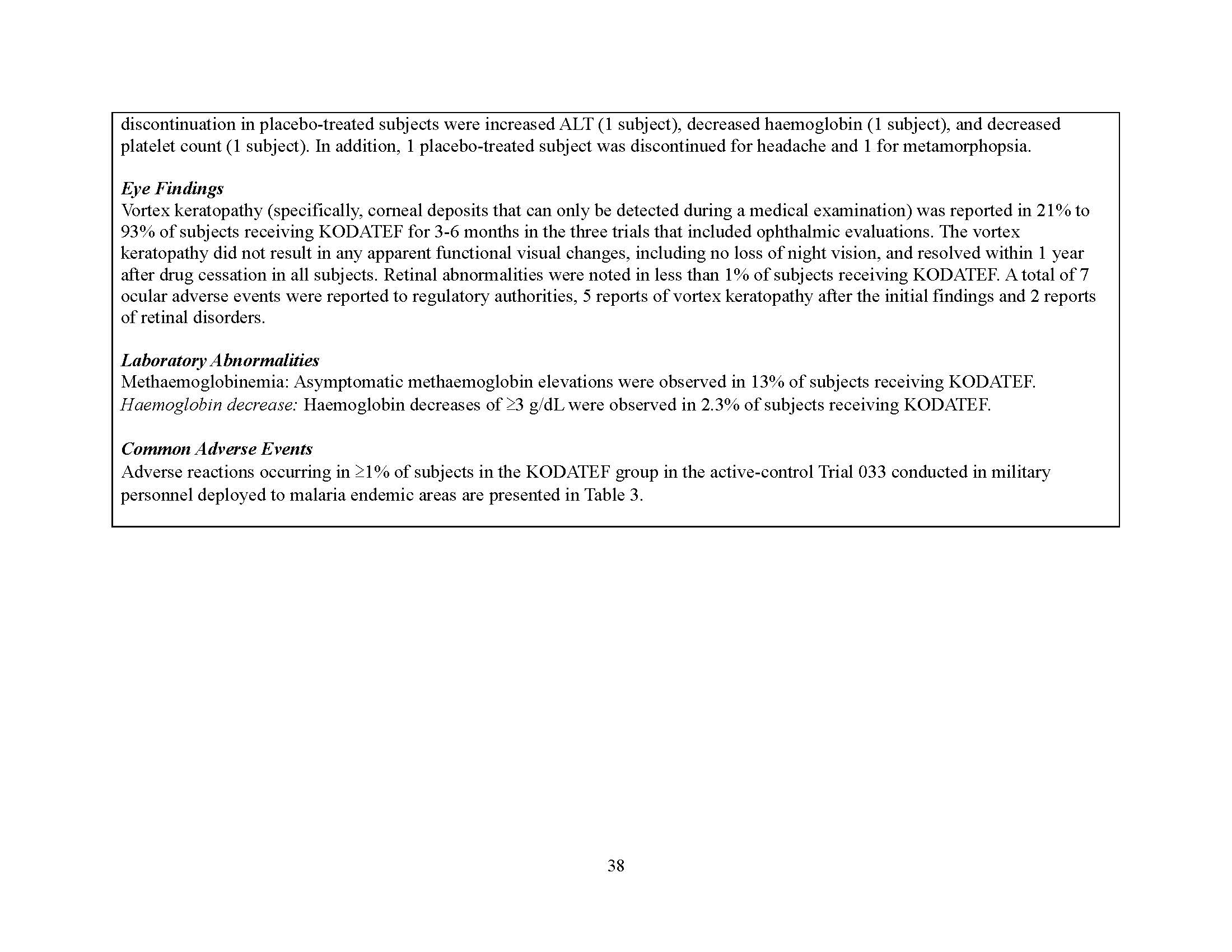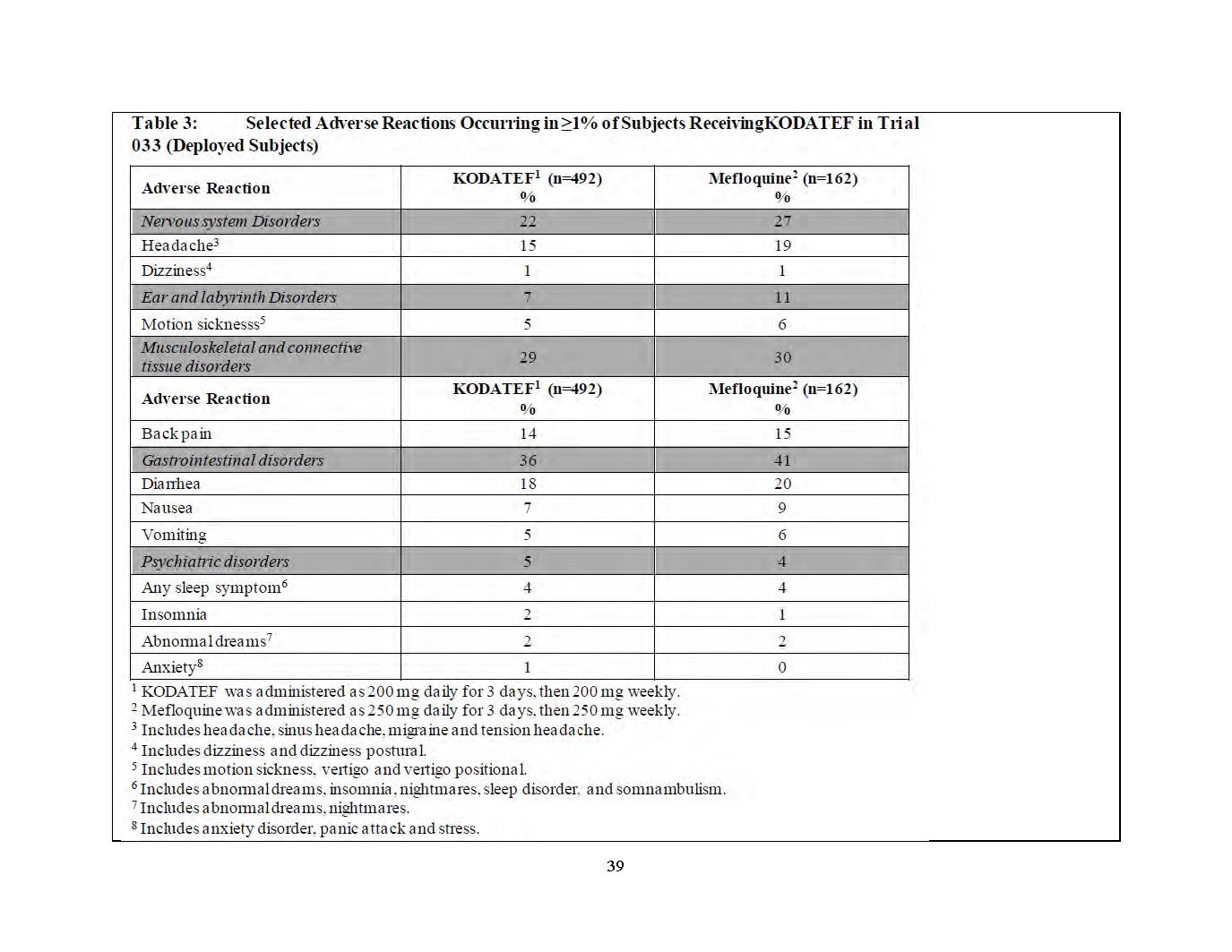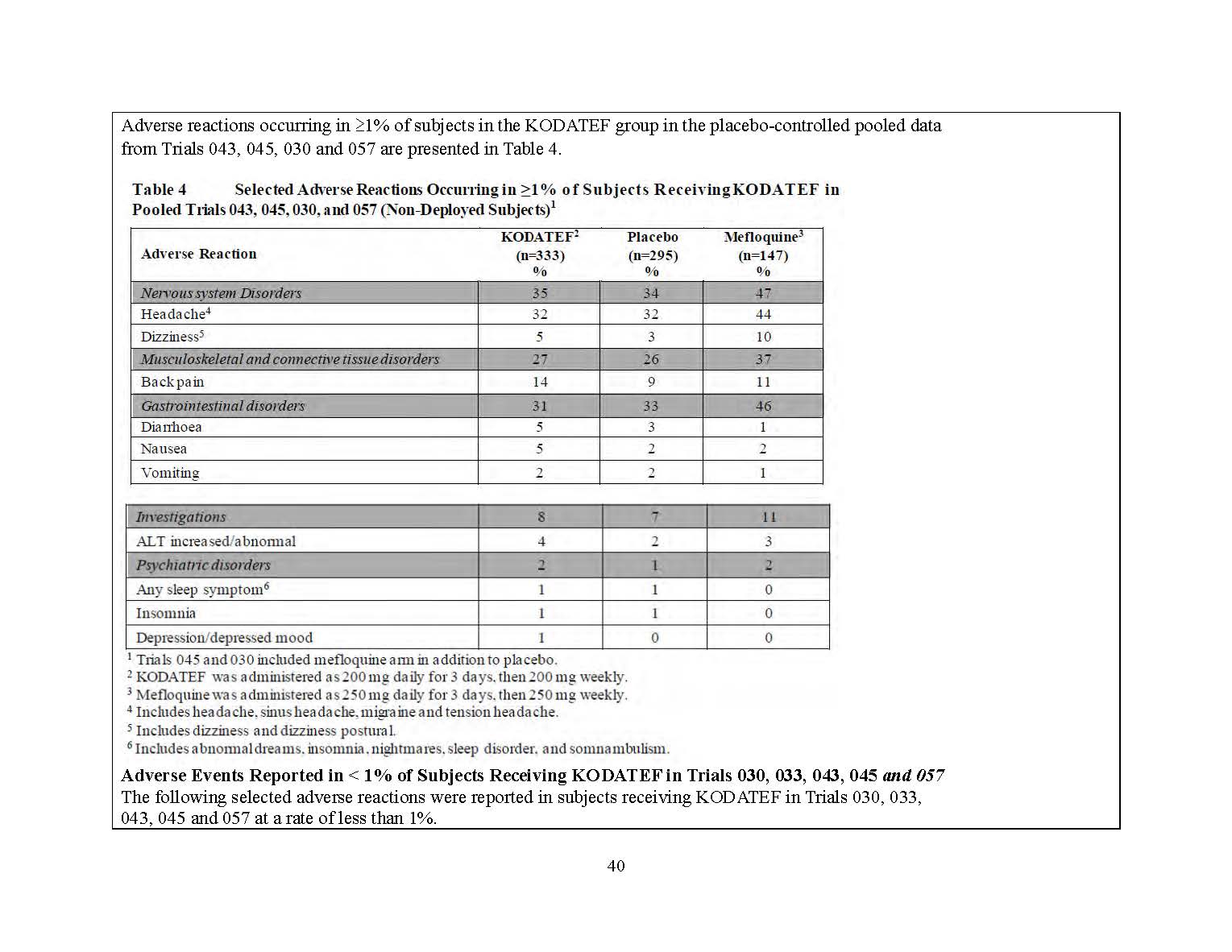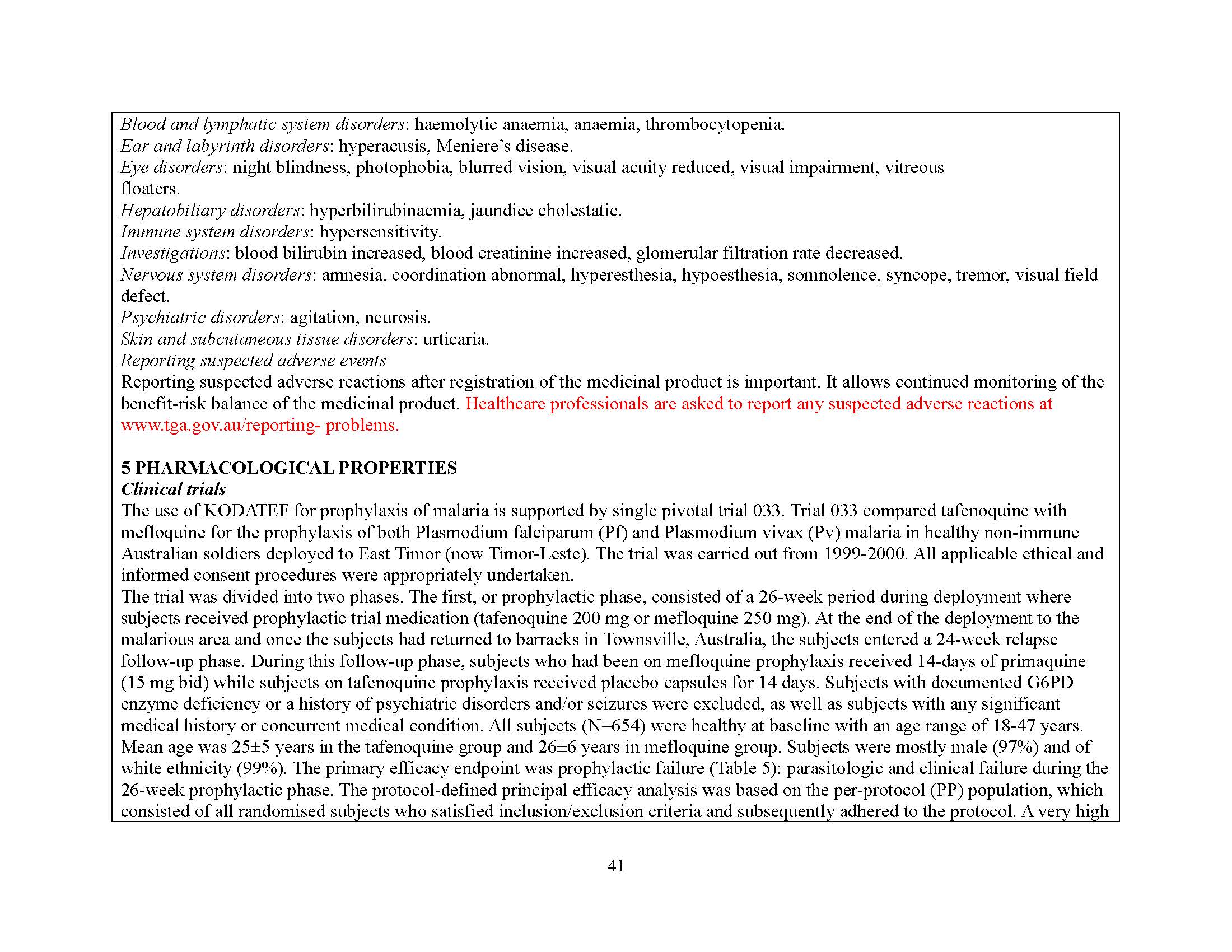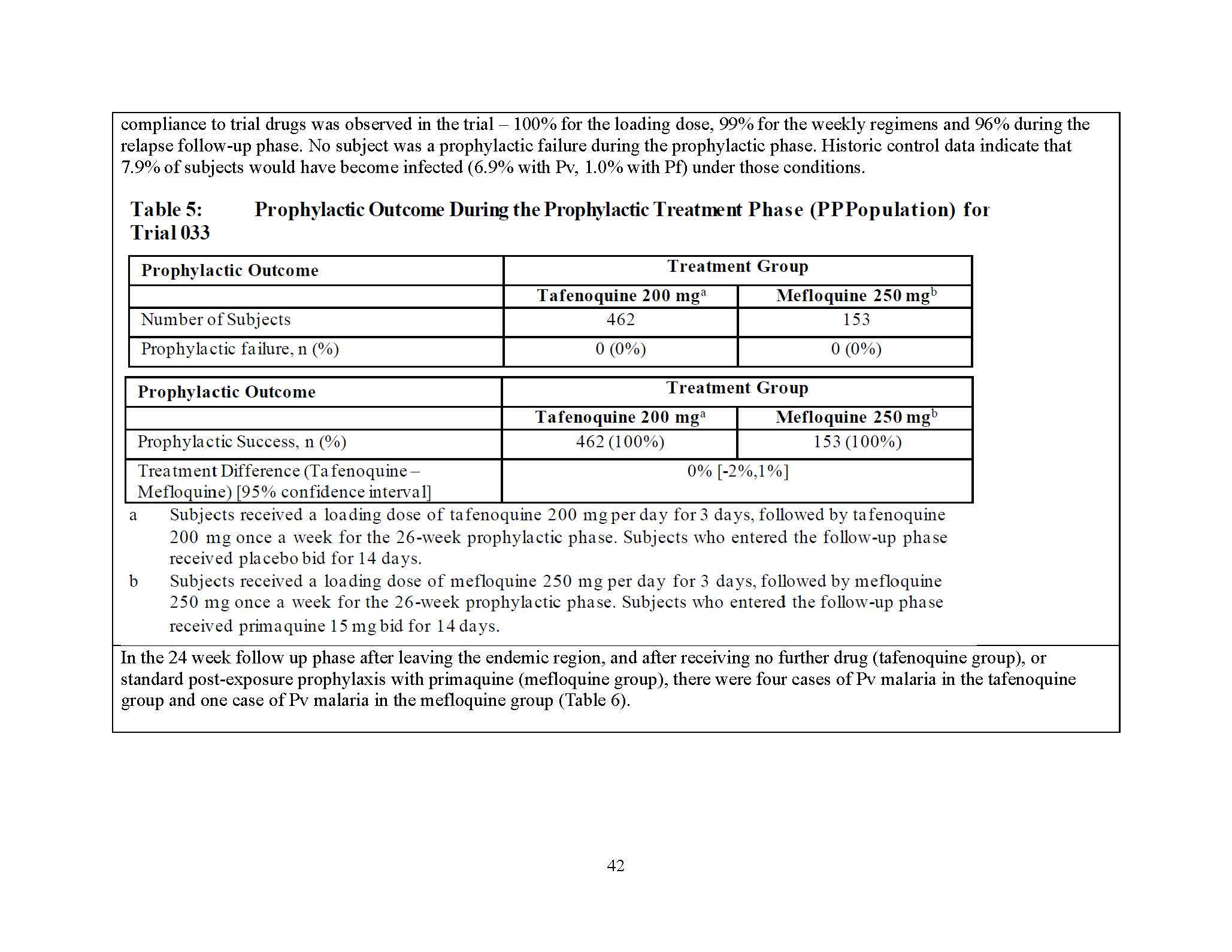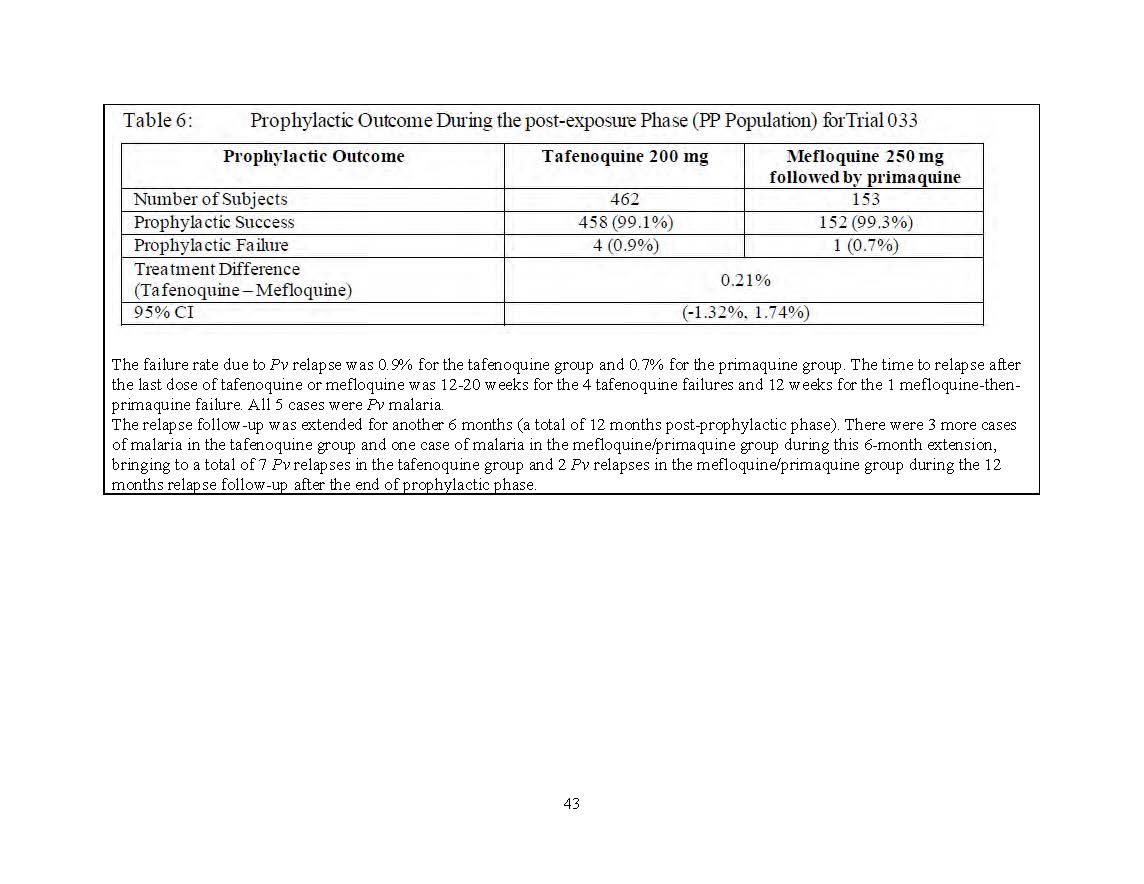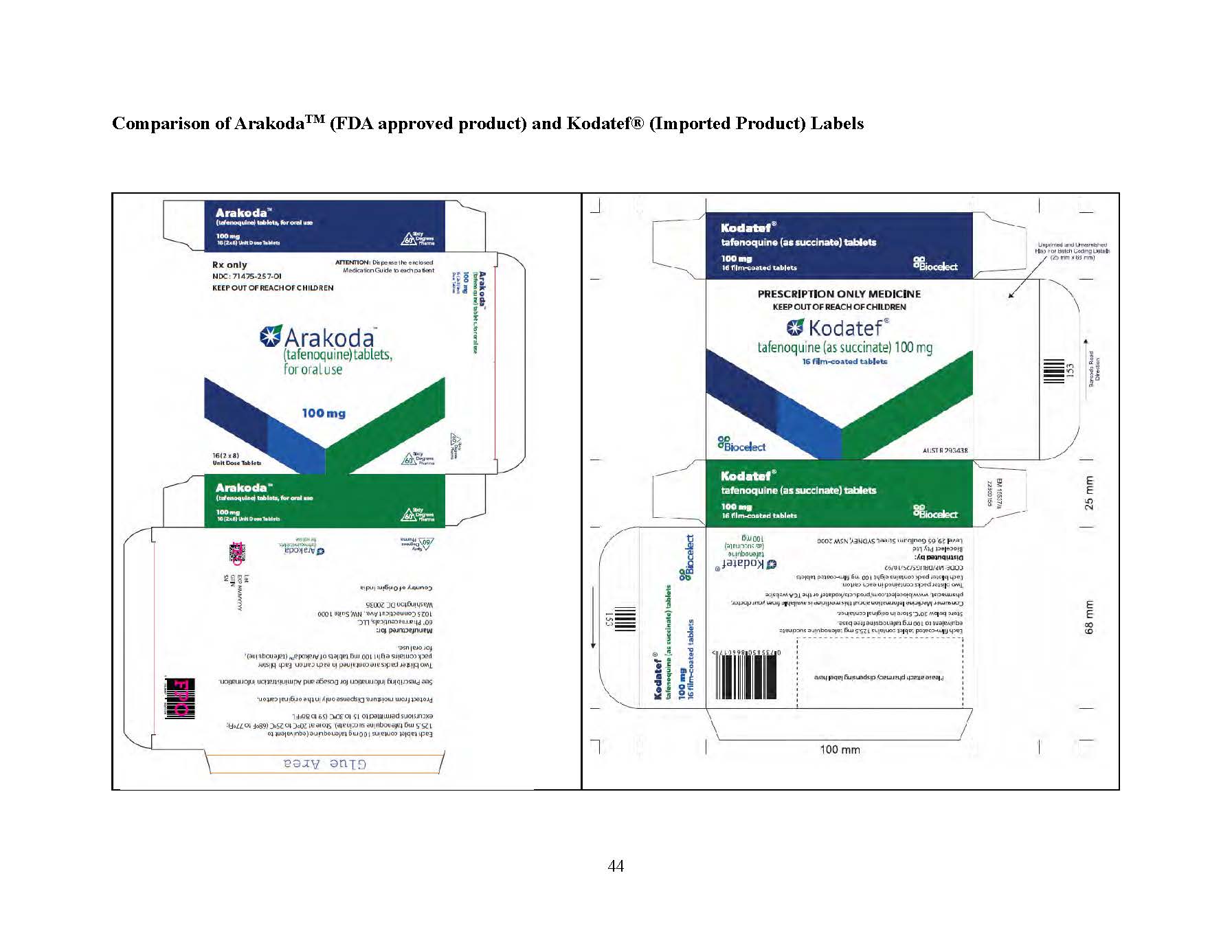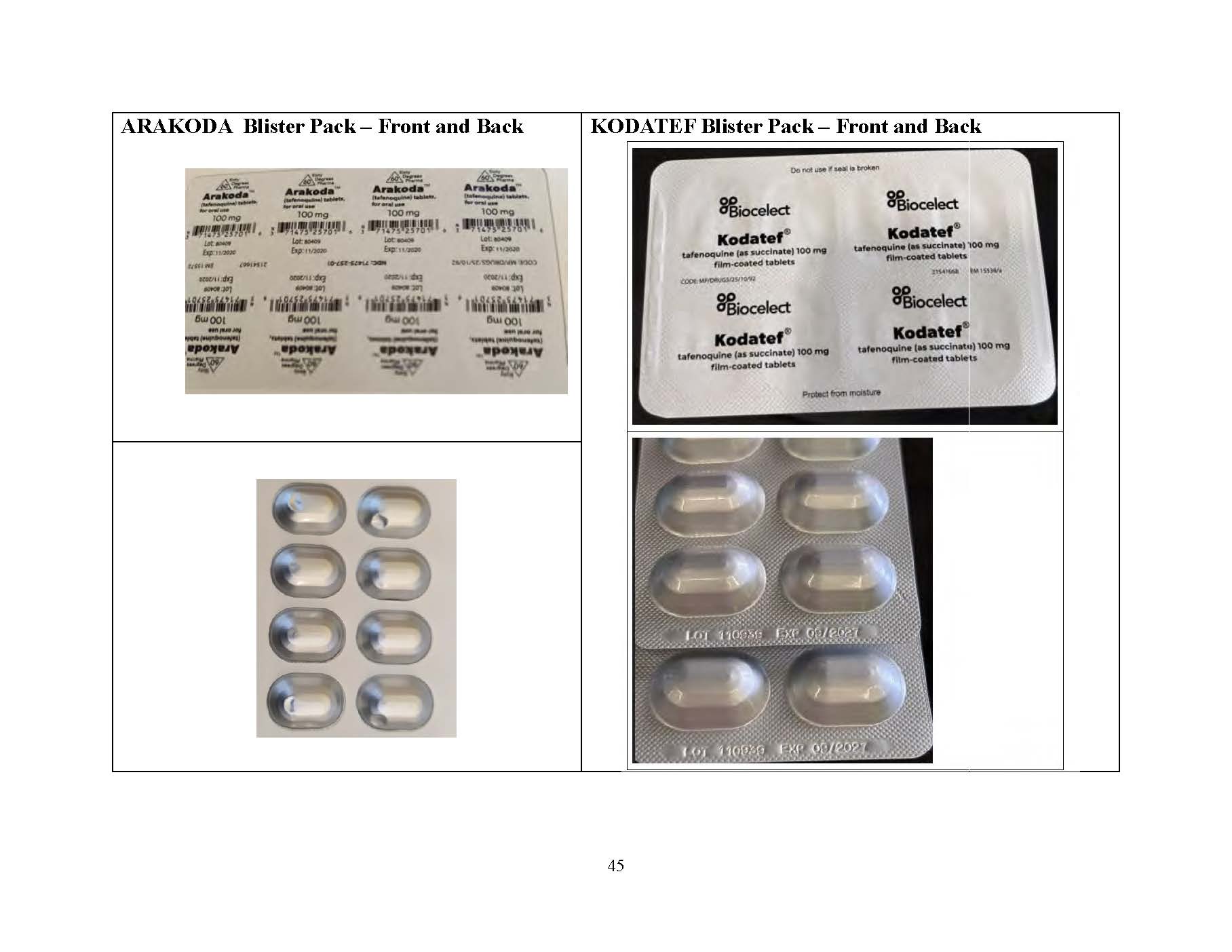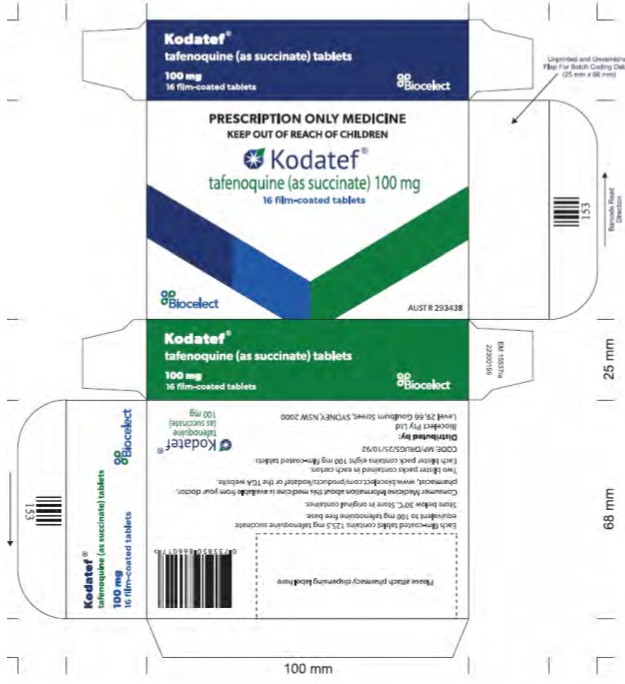 DRUG LABEL: Kodatef
NDC: 71475-258 | Form: TABLET, FILM COATED
Manufacturer: 60 Degrees Pharmaceuticals, INC
Category: prescription | Type: HUMAN PRESCRIPTION DRUG LABEL
Date: 20250210

ACTIVE INGREDIENTS: TAFENOQUINE 100 mg/1 1
INACTIVE INGREDIENTS: TITANIUM DIOXIDE; MANNITOL; MICROCRYSTALLINE CELLULOSE; HYPROMELLOSE 2208 (100 MPA.S); IRON OXIDES; MAGNESIUM STEARATE

WARNINGS AND PRECAUTIONS

Hemolytic Anemia
G6PD Deficiency in Pregnancy and Lactation
Methemoglobinemia
Psychiatric Effects
Hypersensitivity Reactions

Delayed Adverse Reactions, Including Hemolytic Anemia, Methemoglobinemia, Psychiatric Effects, and Hypersensitivity Reactions

Dear Healthcare Provider Letter pages 1-61

DOSAGE AND ADMINISTRATION

Loading Dose: 200 mg (two of the 100 mg filmcoated tablets) once daily for three days.
Maintenance Dose: 200 mg (two of the 100 mg filmcoated tablets) once weekly – start seven days after the last loading dose.

INDICATIONS AND USAGE

Malaria prophylaxis, consistent with the approved use of ARAKODA